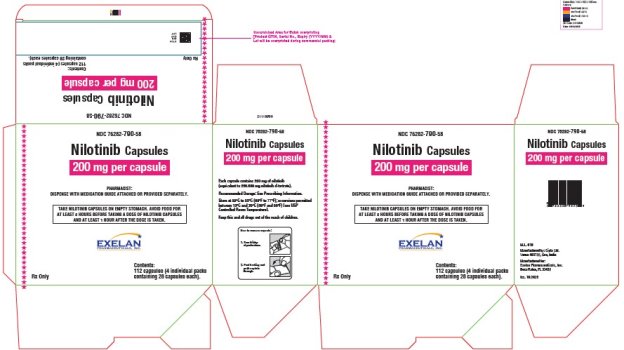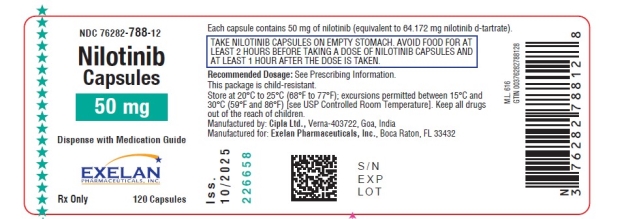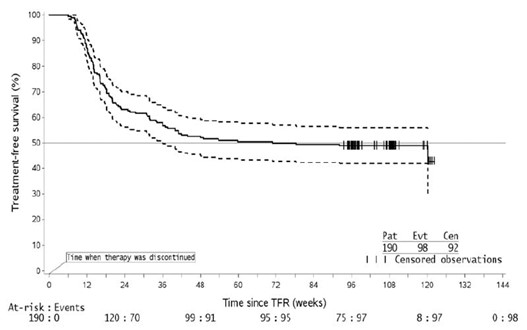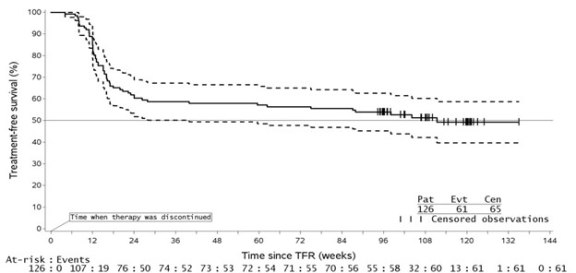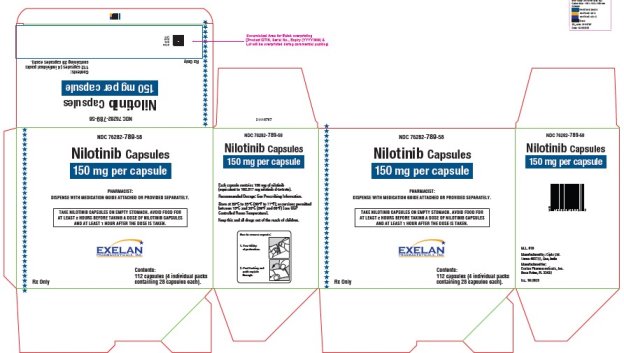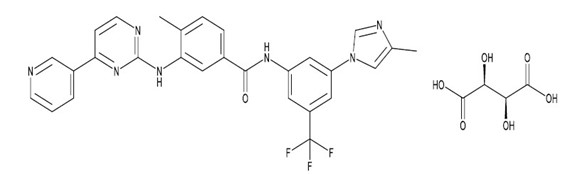 DRUG LABEL: Nilotinib
NDC: 76282-788 | Form: CAPSULE
Manufacturer: EXELAN PHARMACEUTICALS INC.
Category: prescription | Type: HUMAN PRESCRIPTION DRUG LABEL
Date: 20251114

ACTIVE INGREDIENTS: NILOTINIB 50 mg/1 1
INACTIVE INGREDIENTS: SILICON DIOXIDE; CROSPOVIDONE; LACTOSE MONOHYDRATE; MAGNESIUM STEARATE; POLYSORBATE 80; MAGNESIUM ALUMINOMETASILICATE; GELATIN; TITANIUM DIOXIDE; FERRIC OXIDE RED; AMMONIA; FERROSOFERRIC OXIDE; PROPYLENE GLYCOL; POTASSIUM HYDROXIDE; SHELLAC

HIGHLIGHTS OF PRESCRIBING INFORMATION

These highlights do not include all the information needed to use NILOTINIB CAPSULES safely and effectively. See full prescribing information for NILOTINIB CAPSULES. NILOTINIB capsules, for oral use Initial U.S. Approval: 2007

WARNING: QT PROLONGATION and SUDDEN DEATHS

See full prescribing information for complete boxed warning.

- Nilotinib prolongs the QT interval. Prior to Nilotinib Capsules administration and periodically, monitor for hypokalemia or hypomagnesemia and correct deficiencies. (5.2) Obtain ECGs to monitor the QTc at baseline, seven days after initiation, and periodically thereafter, and following any dose adjustments. (5.2, 5.3, 5.7, 5.12)
- Sudden deaths have been reported in patients receiving nilotinib. (5.3) Do not administer Nilotinib Capsules to patients with hypokalemia, hypomagnesemia, or long QT syndrome. (4, 5.2)
- Avoid use of concomitant drugs known to prolong the QT interval and strong CYP3A4 inhibitors. (7.1, 7.2)
- Avoid food 2 hours before and 1 hour after taking the dose. (2.1)

1 INDICATIONS AND USAGE

Nilotinib Capsules is a kinase inhibitor indicated for the treatment of:

- Adult patients with newly diagnosed Philadelphia chromosome positive chronic myeloid leukemia (Ph+ CML) in chronic phase. (1.1)
- Adult patients with chronic phase (CP) and accelerated phase (AP) Ph+ CML resistant to or intolerant to prior therapy that included imatinib. (1.2)

2 DOSAGE AND ADMINISTRATION

- Recommended Adult Dose: Newly diagnosed Ph+ CML-CP: 300 mg orally twice daily. Resistant or intolerant Ph+ CML-CP and CML-AP: 400 mg orally twice daily. (2.1)
- See Dosage and Administration for full dosing instructions and dose-reduction instructions for toxicity. (2.1)
- Reduce starting dose in patients with baseline hepatic impairment. (2.7)
- Eligible newly diagnosed adult patients with Ph+ CML-CP who have received Nilotinib Capsules for a minimum of 3 years and have achieved a sustained molecular response (MR4.5) and patients with Ph+ CML-CP resistant or intolerant to imatinib who have received Nilotinib Capsules for at least 3 years and have achieved a sustained molecular response (MR4.5) may be considered for treatment discontinuation. (2.2, 2.3, 5.16)

3 DOSAGE FORMS AND STRENGTHS

Capsules: 50 mg, 150 mg, and 200 mg of nilotinib (3)

4 CONTRAINDICATIONS

Nilotinib Capsules is contraindicated in patients with,

• hypokalemia (4)

• hypomagnesemia (4)

• long QT syndrome (4)

5 WARNINGS AND PRECAUTIONS

- Myelosuppression: Monitor complete blood count (CBC) during therapy and manage by treatment interruption or dose reduction. (5.1)
- Cardiac and Arterial Vascular Occlusive Events: Evaluate cardiovascular status, monitor and manage cardiovascular risk factors during Nilotinib Capsules therapy. (5.4)
- Pancreatitis and Elevated Serum Lipase: Monitor serum lipase; if elevations are accompanied by abdominal symptoms, interrupt doses and consider appropriate diagnostics to exclude pancreatitis. (5.5)
- Hepatotoxicity: Monitor hepatic function tests monthly or as clinically indicated. (5.6)
- Electrolyte Abnormalities: Nilotinib Capsules can cause hypophosphatemia, hypokalemia, hyperkalemia, hypocalcemia, and hyponatremia. Correct electrolyte abnormalities prior to initiating Nilotinib Capsules and monitor periodically during therapy. (5.7)
- Tumor Lysis Syndrome: Maintain adequate hydration and correct uric acid levels prior to initiating therapy with Nilotinib Capsules. (5.8)
- Hemorrhage: Hemorrhage from any site may occur. Advise patients to report signs and symptoms of bleeding and medically manage as needed. (5.9)
- Fluid Retention: Monitor patients for unexpected rapid weight gain, swelling, and shortness of breath. Manage medically. (5.13)
- Effects on Growth and Development in Pediatric Patients: Growth retardation has been reported in pediatric patients treated with nilotinib. Monitor growth and development in pediatric patients. (5.14)
- Embryo-Fetal Toxicity: Can cause fetal harm. Advise females of reproductive potential of potential risk to a fetus and to use effective contraception. (5.15, 8.1, 8.3)
- Treatment Discontinuation: Patients must have typical BCR-ABL transcripts. An FDA-authorized test with a detection limit below MR4.5 must be used to determine eligibility for discontinuation. Patients must be frequently monitored by the FDA authorized test to detect possible loss of remission. (5.16)

6 ADVERSE REACTIONS

The most commonly reported non-hematologic adverse reactions (≥ 20%) in adult patients are nausea, rash, headache, fatigue, pruritus, vomiting, diarrhea, cough, constipation, arthralgia, nasopharyngitis, pyrexia, and night sweats. Hematologic adverse drug reactions include myelosuppression: thrombocytopenia, neutropenia, and anemia. (6.1)

To report SUSPECTED ADVERSE REACTIONS, contact Cipla Ltd. at 1-866-604-3268 or FDA at 1-800-FDA-1088 or www.fda.gov/medwatch.

7 DRUG INTERACTIONS

- Strong CYP3A Inhibitors: Avoid concomitant use with Nilotinib Capsules or reduce Nilotinib Capsules dose if concomitant use cannot be avoided. (7.1)
- Strong CYP3A Inducers: Avoid concomitant use with Nilotinib Capsules. (7.1)
- Proton Pump Inhibitors: Use short-acting antacids or H2 blockers as an alternative to proton pump inhibitors. (7.1)

8 USE IN SPECIFIC POPULATIONS

- Lactation: Advise women not to breastfeed. (8.2)

Additional pediatric use information is approved for Novartis Pharmaceuticals Corporation’s Tasigna® (nilotinib) capsules. However, due to Novartis Pharmaceuticals Corporation’s marketing exclusivity rights, this drug product is not labeled with that pediatric information

FULL PRESCRIBING INFORMATION

WARNING: QT PROLONGATION and SUDDEN DEATHS

- Nilotinib prolongs the QT interval. Prior to Nilotinib Capsules administration and periodically, monitor for hypokalemia or hypomagnesemia and correct deficiencies [see Warnings and Precautions (5.2)]. Obtain ECGs to monitor the QTc at baseline, seven days after initiation, and periodically thereafter, and following any dose adjustments [see Warnings and Precautions (5.2, 5.3, 5.7, 5.12)].
- Sudden deaths have been reported in patients receiving nilotinib [see Warnings and Precautions (5.3)]. Do not administer Nilotinib Capsules to patients with hypokalemia, hypomagnesemia, or long QT syndrome [see Contraindications (4), Warnings and Precautions (5.2)].
- Avoid use of concomitant drugs known to prolong the QT interval and strong CYP3A4 inhibitors [see Drug Interactions (7.1, 7.2)].
- Avoid food 2 hours before and 1 hour after taking the dose [see Dosage and Administration (2.1)].

1 INDICATIONS AND USAGE

1.1 Adult Patients With Newly Diagnosed Ph+ CML-CP

Nilotinib Capsules is indicated for the treatment of adult patients with newly diagnosed Philadelphia chromosome positive chronic myeloid leukemia (Ph+ CML) in chronic phase.

Additional pediatric use information is approved for Novartis Pharmaceuticals Corporation’s Tasigna® (nilotinib) capsules. However, due to Novartis Pharmaceuticals Corporation’s marketing exclusivity rights, this drug product is not labeled with that pediatric information.

1.2 Adult Patients With Resistant or Intolerant Ph+ CML-CP and CML-AP

Nilotinib Capsules is indicated for the treatment of adult patients with chronic phase and accelerated phase Philadelphia chromosome positive chronic myelogenous leukemia (Ph+ CML) resistant or intolerant to prior therapy that included imatinib.

Additional pediatric use information is approved for Novartis Pharmaceuticals Corporation’s Tasigna® (nilotinib) capsules. However, due to Novartis Pharmaceuticals Corporation’s marketing exclusivity rights, this drug product is not labeled with that pediatric information.

2 DOSAGE AND ADMINISTRATION

2.1 Recommended Dosage

Dosage in Adult Patients with Newly Diagnosed Ph+ CML-CP

The recommended dosage of Nilotinib Capsules is 300 mg orally twice daily.

Dosage in Adult Patients with Resistant or Intolerant Ph+ CML-CP and CML-AP

The recommended dosage of Nilotinib Capsules is 400 mg orally twice daily.

Additional Administration Instructions

Dose Nilotinib Capsules twice daily at approximately 12-hour intervals on an empty stomach. No food should be consumed for at least 2 hours before the dose is taken and for at least 1 hour after the dose is taken. Advise patients to swallow the capsules whole with water and not open the capsules [see Boxed Warning, Clinical Pharmacology (12.3)]. If a dose of Nilotinib Capsules is missed, the patient should take the next scheduled dose at its regular time. The patient should not take two doses at the same time.

Optional Concomitant Therapy

Nilotinib Capsules may be given in combination with hematopoietic growth factors, such as erythropoietin or G-CSF if clinically indicated. Nilotinib Capsules may be given with hydroxyurea or anagrelide if clinically indicated.

Additional pediatric use information is approved for Novartis Pharmaceuticals Corporation’s Tasigna® (nilotinib) capsules. However, due to Novartis Pharmaceuticals Corporation’s marketing exclusivity rights, this drug product is not labeled with that pediatric information.

2.2 Discontinuation of Treatment After a Sustained Molecular Response (MR4.5) on Nilotinib Capsules

Patient Selection

Eligibility for Discontinuation of Treatment

Ph+ CML-CP patients with typical BCR-ABL transcripts, who have been taking Nilotinib Capsules for a minimum of 3 years and have achieved a sustained molecular response (MR4.5, corresponding to = BCR-ABL/ABL ≤ 0.0032% IS), may be eligible for treatment discontinuation [see Clinical Studies (14.3, 14.4)]. Information on FDA authorized tests for the detection and quantitation of BCR-ABL transcripts to determine eligibility for treatment discontinuation is available at http://www.fda.gov/CompanionDiagnostics.

Patients with typical BCR-ABL transcripts (e13a2/b2a2 or e14a2/b3a2), who achieve the sustained MR4.5 criteria, are eligible for discontinuation of Nilotinib Capsules. Patients must continue to be monitored for possible loss of molecular remission after treatment discontinuation. Use the same FDA-authorized test to consistently monitor molecular response levels while on and off treatment.

Consider discontinuation in patients with newly diagnosed Ph+ CML-CP who have:

- been treated with Nilotinib Capsules for at least 3 years
- maintained a molecular response of at least MR4.0 (corresponding to = BCR-ABL/ABL ≤ 0.01% IS) for one year prior to discontinuation of therapy
- achieved an MR4.5 for the last assessment taken immediately prior to discontinuation of therapy
- been confirmed to express the typical BCR-ABL transcripts (e13a2/b2a2 or e14a2/b3a2)
- no history of accelerated phase or blast crisis
- no history of prior attempts of treatment-free remission discontinuation that resulted in relapse.

Consider discontinuation in patients with Ph+ CML-CP that are resistant or intolerant to imatinib who have achieved a sustained molecular response (MR4.5) on Nilotinib Capsules who have:

- been treated with Nilotinib Capsules for a minimum of 3 years
- been treated with imatinib only prior to treatment with Nilotinib Capsules
- achieved a molecular response of MR4.5 (corresponding to = BCR-ABL/ABL ≤ 0.0032% IS)
- sustained an MR4.5 for a minimum of one year immediately prior to discontinuation of therapy
- been confirmed to express the typical BCR-ABL transcripts (e13a2/b2a2 or e14a2/b3a2)
- no history of accelerated phase or blast crisis
- no history of prior attempts of treatment-free remission discontinuation that resulted in relapse.

Monitor BCR-ABL transcript levels and complete blood count (CBC) with differential in patients who have discontinued Nilotinib Capsules therapy monthly for one year, then every 6 weeks for the second year, and every 12 weeks thereafter [see Warnings and Precautions (5.16)].

Upon the loss of MR4.0 (corresponding to = BCR-ABL/ABL ≤ 0.01% IS) during the treatment-free phase, monitor BCR-ABL transcript levels every 2 weeks until BCR-ABL levels remain lower than major molecular response [(MMR), corresponding to MR3.0 or = BCR-ABL/ABL ≤ 0.1% IS] for 4 consecutive measurements. The patient can then proceed to the original monitoring schedule.

2.3 Reinitiation of Treatment in Patients Who Lose Molecular Response After Discontinuation of Therapy With Nilotinib Capsules

- Newly diagnosed patients who lose MMR must reinitiate treatment within 4 weeks at the dose level prior to discontinuation of therapy [see Warnings and Precautions (5.16)]. Patients who reinitiate Nilotinib Capsules therapy should have their BCR-ABL transcript levels monitored monthly until major molecular response is re-established and every 12 weeks thereafter.
- Patients resistant or intolerant to prior treatment that included imatinib with confirmed loss of MR4.0 (2 consecutive measures separated by at least 4 weeks showing loss of MR4.0) or loss of MMR must reinitiate treatment within 4 weeks at the dose level prior to discontinuation of therapy [see Warnings and Precautions (5.16)]. Patients who reinitiate Nilotinib Capsules therapy should have their BCR-ABL transcript levels monitored monthly until previous major molecular response or MR4.0 is re-established and every 12 weeks thereafter.

2.4 Dosage Modification for QT Interval Prolongation

See Table 2 for dose adjustments for QT interval prolongation [see Warnings and Precautions (5.2), Clinical Pharmacology (12.2)].

Table 2: Dosage Adjustments for Adult Patients With QT Prolongation

Degree of QTc prolongation | Dosage adjustment
ECGs with a QTc greater than 480 msec | 1. Withhold Nilotinib Capsules, and perform an analysis of serum potassium and magnesium, and if below lower limit of normal, correct with supplements to within normal limits. Concomitant medication usage must be reviewed. 2. Resume within 2 weeks at prior dose if QTcF returns to less than 450 msec and to within 20 msec of baseline. 3. If QTcF is between 450 msec and 480 msec after 2 weeks, reduce the dose to 400 mg once daily in adults. 4. Discontinue Nilotinib Capsules if, following dose-reduction to 400 mg once daily in adults, QTcF returns to greater than 480 msec. 5. An ECG should be repeated approximately 7 days after any dose adjustment.
Abbreviation: ECG, electrocardiogram.

Additional pediatric use information is approved for Novartis Pharmaceuticals Corporation’s Tasigna® (nilotinib) capsules. However, due to Novartis Pharmaceuticals Corporation’s marketing exclusivity rights, this drug product is not labeled with that pediatric information.

2.5 Dosage Modifications for Myelosuppression

Withhold or reduce Nilotinib Capsules dosage for hematological toxicities (neutropenia, thrombocytopenia) that are not related to underlying leukemia (Table 3) [see Warnings and Precautions (5.1)].

Table 3: Dosage Adjustments for Neutropenia and Thrombocytopenia

Diagnosis | Degree of myelosuppression | Dosage adjustment
Adult patients with:; - Newly diagnosed Ph+ CML in chronic phase at 300 mg twice daily - Resistant or intolerant Ph+ CML in chronic phase or accelerated phase at 400 mg twice daily | ANC less than 1 x 10^9/L and/or platelet counts less than 50 x 10^9/L | 1. Stop Nilotinib Capsules, and monitor blood counts. 2. Resume within 2 weeks at prior dose if ANC greater than 1 x 10^9/L and platelets greater than 50 x 10^9/L. 3. If blood counts remain low for greater than 2 weeks, reduce the dose to 400 mg once daily.
Abbreviations: ANC, absolute neutrophil count; Ph+ CML, Philadelphia chromosome positive chronic myeloid leukemia.

Additional pediatric use information is approved for Novartis Pharmaceuticals Corporation’s Tasigna® (nilotinib) capsules. However, due to Novartis Pharmaceuticals Corporation’s marketing exclusivity rights, this drug product is not labeled with that pediatric information.

2.6 Dosage Modifications for Selected Non-Hematologic Laboratory Abnormalities and Other Toxicities

See Table 4 for dosage adjustments for elevations of lipase, amylase, bilirubin, and/or hepatic transaminases [see Warnings and Precautions (5.5, 5.6), Adverse Reactions (6.1)].

Table 4: Dosage Adjustments for Selected Non-Hematologic Laboratory Abnormalities

Degree of non-hematologic laboratory abnormality | Dosage adjustment
Elevated serum | Adult patients:; 1. Withhold Nilotinib Capsules and monitor serum lipase or amylase.; 2. Resume treatment at 400 mg once daily if serum lipase or amylase returns to less than or equal to Grade 1.
lipase or amylase greater than or | Adult patients:; 1. Withhold Nilotinib Capsules and monitor serum lipase or amylase.; 2. Resume treatment at 400 mg once daily if serum lipase or amylase returns to less than or equal to Grade 1.
equal to Grade 3 | Adult patients:; 1. Withhold Nilotinib Capsules and monitor serum lipase or amylase.; 2. Resume treatment at 400 mg once daily if serum lipase or amylase returns to less than or equal to Grade 1.
Elevated bilirubin | Adult patients:; 1. Withhold Nilotinib Capsules and monitor bilirubin.; 2. Resume treatment at 400 mg once daily if bilirubin returns to less than or equal to Grade 1.
greater than or equal to Grade 3 | Adult patients:; 1. Withhold Nilotinib Capsules and monitor bilirubin.; 2. Resume treatment at 400 mg once daily if bilirubin returns to less than or equal to Grade 1.
in adult patients | Adult patients:; 1. Withhold Nilotinib Capsules and monitor bilirubin.; 2. Resume treatment at 400 mg once daily if bilirubin returns to less than or equal to Grade 1.
 | Adult patients:; 1. Withhold Nilotinib Capsules and monitor bilirubin.; 2. Resume treatment at 400 mg once daily if bilirubin returns to less than or equal to Grade 1.
Elevated hepatic | Adult patients:; 1. Withhold Nilotinib Capsules and monitor hepatic transaminases.; 2. Resume treatment at 400 mg once daily if hepatic transaminases returns to less than or equal to Grade 1.
transaminases | Adult patients:; 1. Withhold Nilotinib Capsules and monitor hepatic transaminases.; 2. Resume treatment at 400 mg once daily if hepatic transaminases returns to less than or equal to Grade 1.
greater than or equal to Grade 3 | Adult patients:; 1. Withhold Nilotinib Capsules and monitor hepatic transaminases.; 2. Resume treatment at 400 mg once daily if hepatic transaminases returns to less than or equal to Grade 1.

If clinically significant moderate or severe non-hematologic toxicity develops (including medically severe fluid retention), see Table 5 for dosage adjustments [see Adverse Reactions (6.1)].

Table 5: Dosage Adjustments for Other Non-Hematologic Toxicities

Degree of “other Non-hematologic toxicity” | Dosage adjustment
Other clinically moderate or severe non-hematologic toxicity | Adult patients:
Other clinically moderate or severe non-hematologic toxicity | 1. Withhold Nilotinib Capsules until toxicity has resolved. 2. Resume treatment at 400 mg once daily if previous dose was 300 mg twice daily in adult patients newly diagnosed with CML-CP or 400 mg twice daily in adult patients with resistant or intolerant CML-CP and CML-AP. 3. Discontinue treatment if the prior dose was 400 mg once daily in adult patients. 4. If clinically appropriate, consider re-escalation of the dose to 300 mg (newly diagnosed Ph+ CML-CP) or 400 mg (resistant or intolerant Ph+ CML-CP and CML-AP) twice daily.
Abbreviations: CML-AP, chronic myeloid leukemia-accelerated phase; CML-CP, chronic myeloid leukemia-chronic phase; Ph+, Philadelphia chromosome positive.

Additional pediatric use information is approved for Novartis Pharmaceuticals Corporation’s Tasigna® (nilotinib) capsules. However, due to Novartis Pharmaceuticals Corporation’s marketing exclusivity rights, this drug product is not labeled with that pediatric information.

2.7 Recommended Nilotinib Capsules Dosage in Patients with Hepatic Impairment

If possible, consider alternative therapies. If Nilotinib Capsules must be administered to patients with hepatic impairment, the recommended Nilotinib Capsules dosage is provided in Table 6 [see Use in Specific Populations (8.7)].

Table 6: Dose Adjustments for Adult Patients With Hepatic Impairment

Diagnosis | Degree of hepatic impairment | Dosage adjustment
Newly diagnosed Ph+ CML in chronic phase | Mild (Child-Pugh A), Moderate (Child-Pugh B), or Severe (Child-Pugh C) | Reduce Nilotinib Capsules dosage to 200 mg twice daily.; Increase Nilotinib Capsules dosage to 300 mg twice daily based on tolerability.
Resistant or intolerant Ph+ CML in chronic phase or accelerated phase | Mild or Moderate | Reduce Nilotinib Capsules dosage to 300 mg twice daily.; Increase Nilotinib Capsules dosage to 400 mg twice daily based on tolerability.
Resistant or intolerant Ph+ CML in chronic phase or accelerated phase | Severe | Reduce Nilotinib Capsules dosage to 200 mg twice daily.; Increase Nilotinib Capsules dosage to 300 mg twice daily and then to 400 mg twice daily based on tolerability.

2.8 Dosage Modification for Strong CYP3A4 Inhibitors

Avoid the concomitant use of strong CYP3A4 inhibitors. If concomitant use is required, reduce Nilotinib Capsules dosage to 300 mg once daily in patients with resistant or intolerant Ph+ CML or to 200 mg once daily in patients with newly diagnosed Ph+ CML-CP. If the strong inhibitor is discontinued, allow a washout period of 5 half-lives before adjusting Nilotinib Capsules dose upward to the indicated dose. For patients who cannot avoid use of strong CYP3A4 inhibitors, monitor closely for prolongation of the QT interval [see Boxed Warning, Warnings and Precautions (5.2), Drug Interactions (7.1, 7.2), Clinical Pharmacology (12.3)].

3 DOSAGE FORMS AND STRENGTHS

Capsules:

- 50 mg: light yellow colored blend filled in hard gelatin capsule size 4 cap red opaque linear imprinted with 'Cipla' in black ink and body white opaque linear imprinted with ‘030 50 mg’ in black ink. Each capsule contains the equivalent of 50 mg of nilotinib.

- 150 mg: light yellow colored blend filled in hard gelatin capsule size 1, cap red opaque linear imprinted with 'Cipla' in black ink and body red opaque linear imprinted with ‘031 150 mg’ in black ink. Each capsule contains the equivalent of 150 mg of nilotinib.

- 200 mg: light yellow colored blend filled in hard gelatin capsule size 0, cap white opaque linear imprinted with ‘Cipla’ in black ink and body white opaque linear imprinted with ‘032 200 mg’ in black ink. Each capsule contains the equivalent of 200 mg of nilotinib.

4 CONTRAINDICATIONS

Nilotinib Capsules is contraindicated in patients with hypokalemia, hypomagnesemia, or long QT syndrome [see Boxed Warning and Warnings and Precautions (5.2)].

5 WARNINGS AND PRECAUTIONS

5.1 Myelosuppression

Treatment with Nilotinib Capsules can cause Grade 3/4 thrombocytopenia, neutropenia, and anemia. Perform CBCs every 2 weeks for the first 2 months and then monthly thereafter, or as clinically indicated. Myelosuppression was generally reversible and usually managed by withholding Nilotinib Capsules temporarily or dose reduction [see Dosage and Administration (2.5)].

5.2 QT Prolongation

Nilotinib has been shown to prolong cardiac ventricular repolarization as measured by the QT interval on the surface electrocardiogram (ECG) in a concentration-dependent manner [see Adverse Reactions (6.1), Clinical Pharmacology (12.2)]. Prolongation of the QT interval can result in a type of ventricular tachycardia called torsade de pointes, which may result in syncope, seizure, and/or death. Electrocardiograms should be performed at baseline, 7 days after initiation of Nilotinib Capsules, and periodically as clinically indicated and following dose adjustments [see Dosage and Administration (2.4), Warnings and Precautions (5.12)].

Nilotinib Capsules should not be used in patients who have hypokalemia, hypomagnesemia, or long QT syndrome. Before initiating Nilotinib Capsules and periodically, test electrolyte, calcium, and magnesium blood levels. Hypokalemia or hypomagnesemia must be corrected prior to initiating Nilotinib Capsules and these electrolytes should be monitored periodically during therapy [see Warnings and Precautions (5.12)].

Significant prolongation of the QT interval may occur when Nilotinib Capsules is inappropriately taken with food and/or strong CYP3A4 inhibitors and/or medicinal products with a known potential to prolong QT. Therefore, avoid coadministration with food and concomitant Nilotinib Capsules use with strong CYP3A4 inhibitors and/or medicinal products with a known potential to prolong QT should be avoided [see Dosage and Administration (2.1), Drug Interactions (7.1, 7.2)]. The presence of hypokalemia and hypomagnesemia may further prolong the QT interval [see Warnings and Precautions (5.7, 5.12)].

5.3 Sudden Deaths

Sudden deaths have been reported in 0.3% of patients with CML treated with nilotinib in clinical studies of 5661 patients. The relative early occurrence of some of these deaths relative to the initiation of nilotinib suggests the possibility that ventricular repolarization abnormalities may have contributed to their occurrence.

5.4 Cardiac and Arterial Vascular Occlusive Events

Cardiovascular events, including arterial vascular occlusive events, were reported in a randomized, clinical trial in newly diagnosed CML patients and observed in the postmarketing reports of patients receiving nilotinib therapy [see Adverse Reactions (6.1)]. With a median time on therapy of 60 months in the clinical trial, cardiovascular events, including arterial vascular occlusive events, occurred in 9% and 15% of patients in the nilotinib 300 and 400 mg twice daily arms, respectively, and in 3.2% in the imatinib arm. These included cases of cardiovascular events, including ischemic heart disease-related cardiac events (5% and 9% in the nilotinib 300 mg and 400 mg twice daily arms, respectively, and 2.5% in the imatinib arm), peripheral arterial occlusive disease (3.6% and 2.9% in the nilotinib 300 mg and 400 mg twice daily arms, respectively, and 0% in the imatinib arm), and ischemic cerebrovascular events (1.4% and 3.2% in the nilotinib 300 mg and 400 mg twice daily arms, respectively, and 0.7% in the imatinib arm). If acute signs or symptoms of cardiovascular events occur, advise patients to seek immediate medical attention. The cardiovascular status of patients should be evaluated and cardiovascular risk factors should be monitored and actively managed during Nilotinib Capsules therapy according to standard guidelines [see Dosage and Administration (2.4)].

5.5 Pancreatitis and Elevated Serum Lipase

Nilotinib can cause increases in serum lipase [see Adverse Reactions (6.1)]. Patients with a previous history of pancreatitis may be at greater risk of elevated serum lipase. If lipase elevations are accompanied by abdominal symptoms, interrupt dosing and consider appropriate diagnostics to exclude pancreatitis [see Dosage and Administration (2.6)]. Test serum lipase levels monthly or as clinically indicated.

5.6 Hepatotoxicity

Nilotinib may result in hepatotoxicity as measured by elevations in bilirubin, aspartate aminotransferase (AST), alanine aminotransferase (ALT), and alkaline phosphatase. Grade 3-4 elevations of bilirubin, AST, and ALT were reported at a higher frequency in pediatric than in adult patients. Monitor hepatic function tests monthly or as clinically indicated [see Warnings and Precautions (5.12)] and following dose adjustments. [see Dosage and Administration (2.6)].

5.7 Electrolyte Abnormalities

The use of nilotinib can cause hypophosphatemia, hypokalemia, hyperkalemia, hypocalcemia, and hyponatremia. Correct electrolyte abnormalities prior to initiating Nilotinib Capsules and during therapy. Monitor these electrolytes periodically during therapy [see Warnings and Precautions (5.12)].

5.8 Tumor Lysis Syndrome

Tumor lysis syndrome (TLS) cases have been reported in nilotinib treated patients with resistant or intolerant CML. Malignant disease progression, high white blood cell (WBC) counts and/or dehydration were present in the majority of these cases. Due to potential for TLS, maintain adequate hydration and correct uric acid levels prior to initiating therapy with Nilotinib Capsules.

5.9 Hemorrhage

Serious hemorrhagic events, including fatal events, have occurred in patients with CML treated with nilotinib. In a randomized trial in patients with newly diagnosed Ph+ CML in chronic phase comparing nilotinib and imatinib, Grade 3 or 4 hemorrhage occurred in 1.1% of patients in the nilotinib 300 mg twice daily arm, in 1.8% of patients in the nilotinib 400 mg twice daily arm, and 0.4% of patients in the imatinib arm. GI hemorrhage occurred in 2.9% and 5% of patients in the nilotinib 300 mg twice daily and 400 mg twice daily arms and in 1.4% of patients in the imatinib arm, respectively. Grade 3 or 4 events occurred in 0.7% and 1.4% of patients in the nilotinib 300 mg twice daily and 400 mg twice daily arms, respectively, and in no patients in the imatinib arm. Monitor for signs and symptoms of bleeding and medically manage as needed.

5.10 Total Gastrectomy

Since the exposure of nilotinib is reduced in patients with total gastrectomy, perform more frequent monitoring of these patients. Consider dose increase or alternative therapy in patients with total gastrectomy [see Clinical Pharmacology (12.3)].

5.11 Lactose

Since the capsules contain lactose, Nilotinib Capsules is not recommended for patients with rare hereditary problems of galactose intolerance, severe lactase deficiency with a severe degree of intolerance to lactose-containing products, or of glucose-galactose malabsorption.

5.12 Monitoring Laboratory Tests

Complete blood counts should be performed every 2 weeks for the first 2 months and then monthly thereafter. Perform chemistry panels, including electrolytes, calcium, magnesium, liver enzymes, lipid profile, and glucose prior to therapy and periodically. Electrocardiograms should be obtained at baseline, 7 days after initiation and periodically thereafter, as well as following dose adjustments [see Warnings and Precautions (5.2)]. Monitor lipid profiles and glucose periodically during the first year of Nilotinib Capsules therapy and at least yearly during chronic therapy. Should treatment with any HMG-CoA reductase inhibitor (a lipid lowering agent) be needed to treat lipid elevations, evaluate the potential for a drug-drug interaction before initiating therapy as certain HMG-CoA reductase inhibitors are metabolized by the CYP3A4 pathway [see Drug Interactions (7.1)]. Assess glucose levels before initiating treatment with Nilotinib Capsules and monitor during treatment as clinically indicated. If test results warrant therapy, physicians should follow their local standards of practice and treatment guidelines.

5.13 Fluid Retention

In the randomized trial in patients with newly diagnosed Ph+ CML in chronic phase, severe (Grade 3 or 4) fluid retention occurred in 3.9% and 2.9% of patients receiving nilotinib 300 mg twice daily and 400 mg twice daily, respectively, and in 2.5% of patients receiving imatinib. Effusions (including pleural effusion, pericardial effusion, ascites) or pulmonary edema, were observed in 2.2% and 1.1% of patients receiving nilotinib 300 mg twice daily and 400 mg twice daily, respectively, and in 2.1% of patients receiving imatinib. Effusions were severe (Grade 3 or 4) in 0.7% and 0.4% of patients receiving nilotinib 300 mg twice daily and 400 mg twice daily, respectively, and in no patients receiving imatinib. Similar events were also observed in postmarketing reports. Monitor patients for signs of severe fluid retention (e.g., unexpected rapid weight gain or swelling) and for symptoms of respiratory or cardiac compromise (e.g., shortness of breath) during Nilotinib Capsules treatment; evaluate etiology and treat patients accordingly.

5.14 Effects on Growth and Development in Pediatric Patients

Growth retardation has been reported in pediatric patients with Ph+ CML in chronic phase treated with nilotinib. Growth deceleration was more pronounced in children who were less than age 12 at baseline. Monitor growth and development in pediatric patients receiving nilotinib treatment.

Additional pediatric use information is approved for Novartis Pharmaceuticals Corporation’s Tasigna® (nilotinib) capsules. However, due to Novartis Pharmaceuticals Corporation’s marketing exclusivity rights, this drug product is not labeled with that pediatric information.

5.15 Embryo-Fetal Toxicity

Based on findings from animal studies and its mechanism of action, Nilotinib Capsules can cause fetal harm when administered to a pregnant woman. In animal reproduction studies, administration of nilotinib to pregnant rats and rabbits during organogenesis caused adverse developmental outcomes, including embryo-fetal lethality/fetal effects (small renal papilla, fetal edema, and skeletal variations) in rats and increased resorptions of fetuses and fetal skeletal variations in rabbits at maternal area under the curve (AUCs) approximately 2 and 0.5 times, respectively, the AUC in patients receiving the recommended dose.

Advise pregnant women of the potential risk to a fetus. Advise females of reproductive potential to use effective contraception during treatment and for 14 days after the last dose [see Use in Specific Populations (8.1, 8.3), Clinical Pharmacology (12.1)].

5.16 Monitoring of BCR-ABL Transcript Levels

Monitoring of BCR-ABL Transcript Levels in Patients Who Discontinued Nilotinib Capsules

Monitor BCR-ABL transcript levels in patients eligible for treatment discontinuation using an FDA authorized test validated to measure molecular response levels with a sensitivity of at least MR4.5 (BCR-ABL/ABL ≤ 0.0032% IS). In patients who discontinue Nilotinib Capsules therapy, assess BCR-ABL transcript levels monthly for one year, then every 6 weeks for the second year, and every 12 weeks thereafter during treatment discontinuation [see Clinical Studies (14.3,14.4), Dosage and Administration (2.2)].

Newly diagnosed patients must reinitiate Nilotinib Capsules therapy within 4 weeks of a loss of major molecular response [(MMR), corresponding to MR3.0 or = BCR-ABL/ABL ≤ 0.1% IS].

Patients resistant or intolerant to prior treatment which included imatinib must reinitiate Nilotinib Capsules therapy within 4 weeks of a loss of MMR or confirmed loss of MR4.0 (two consecutive measures separated by at least 4 weeks showing loss of MR4.0, corresponding to = BCR-ABL/ABL ≤ 0.01% IS).

For patients who fail to achieve MMR after three months of treatment reinitiation, BCR-ABL kinase domain mutation testing should be performed.

Monitoring of BCR-ABL Transcript Levels in Patients Who Have Reinitiated Therapy After Loss of Molecular Response

Monitor CBC and BCR-ABL transcripts in patients who reinitiate treatment with Nilotinib Capsules due to loss of molecular response quantitation every 4 weeks until a major molecular response is re-established, then every 12 weeks.

6 ADVERSE REACTIONS

The following clinically significant adverse reactions can occur with Nilotinib Capsules and are discussed in greater detail in other sections of labeling:

• Myelosuppression [see Warnings and Precautions (5.1)]

• QT Prolongation [see Boxed Warning, Warnings and Precautions (5.2)]

• Sudden Deaths [see Boxed Warning, Warnings and Precautions (5.3)]

• Cardiac and Arterial Vascular Occlusive Events [see Warnings and Precautions (5.4)]

• Pancreatitis and Elevated Serum Lipase [see Warnings and Precautions (5.5)]

• Hepatotoxicity [see Warnings and Precautions (5.6)]

• Electrolyte Abnormalities [see Boxed Warning, Warnings and Precautions (5.7)]

• Hemorrhage [see Warnings and Precautions (5.9)]

• Fluid Retention [see Warnings and Precautions (5.13)]

6.1 Clinical Trials Experience

Because clinical trials are conducted under widely varying conditions, adverse reaction rates observed in the clinical trials of a drug cannot be directly compared to rates in the clinical trials of another drug and may not reflect the rates observed in practice.

In Adult Patients With Newly Diagnosed Ph+ CML-CP

The data below reflect exposure to nilotinib from a randomized trial in patients with newly diagnosed Ph+ CML in chronic phase treated at the recommended dose of 300 mg twice daily (n = 279). The median time on treatment in the nilotinib 300 mg twice daily group was 61 months (range, 0.1 to 71 months). The median actual dose intensity was 593 mg/day in the nilotinib 300 mg twice daily group.

The most common (greater than 10%) non-hematologic adverse drug reactions were rash, pruritus, headache, nausea, fatigue, alopecia, myalgia, and upper abdominal pain. Constipation, diarrhea, dry skin, muscle spasms, arthralgia, abdominal pain, peripheral edema, vomiting, and asthenia were observed less commonly (less than or equal to 10% and greater than 5%).

Increase in QTcF greater than 60 msec from baseline was observed in 1 patient (0.4%) in the 300 mg twice daily treatment group. No patient had an absolute QTcF of greater than 500 msec while on study drug.

The most common hematologic adverse drug reactions (all Grades) were myelosuppression, including: thrombocytopenia (18%), neutropenia (15%), and anemia (8%). See Table 9 for Grade 3/4 laboratory abnormalities.

Discontinuation due to adverse reactions, regardless of relationship to study drug, was observed in 10% of patients.

In Adult Patients With Resistant or Intolerant Ph+ CML-CP and CML-AP

In the single-arm, open-label multicenter clinical trial, a total of 458 patients with Ph+ CML-CP and CML-AP resistant to or intolerant to at least one prior therapy, including imatinib were treated (CML-CP = 321; CML-AP = 137) at the recommended dose of 400 mg twice daily.

The median duration of exposure in days for CML-CP and CML-AP patients is 561 (range, 1 to 1096) and 264 (range, 2 to 1160), respectively.

The median cumulative duration in days of dose interruptions for the CML-CP patients was 20 (range, 1 to 345), and the median duration in days of dose interruptions for the CML-AP patients was 23 (range, 1 to 234).

In patients with CML-CP, the most commonly reported non-hematologic adverse drug reactions (greater than or equal to 10%) were rash, pruritus, nausea, fatigue, headache, constipation, diarrhea, vomiting, and myalgia. The common serious drug-related adverse reactions (greater than or equal to 1% and less than 10%) were thrombocytopenia, neutropenia, and anemia.

In patients with CML-AP, the most commonly reported non-hematologic adverse drug reactions (greater than or equal to 10%) were rash, pruritus and fatigue. The common serious adverse drug reactions (greater than or equal to 1% and less than 10%) were thrombocytopenia, neutropenia, febrile neutropenia, pneumonia, leukopenia, intracranial hemorrhage, elevated lipase, and pyrexia.

Sudden deaths and QT prolongation were reported. The maximum mean QTcF change from baseline at steady-state was 10 msec. Increase in QTcF greater than 60 msec from baseline was observed in 4.1% of the patients and QTcF of greater than 500 msec was observed in 4 patients (less than 1%) [see Boxed Warning, Warnings and Precautions (5.2, 5.3), Clinical Pharmacology (12.2)].

Discontinuation due to adverse drug reactions was observed in 16% of CML-CP and 10% of CML-AP patients.

Most Frequently Reported Adverse Reactions

Tables 7 and 8 show the percentage of adult patients experiencing non-hematologic adverse reactions (excluding laboratory abnormalities) regardless of relationship to study drug. Adverse reactions reported in greater than 10% of adult patients who received at least 1 dose of nilotinib are listed.

Table 7: Most Frequently Reported Non-Hematologic Adverse Reactions (Regardless of Relationship to Study Drug) in Adult Patients With Newly Diagnosed Ph+ CML-CP (greater than or equal to 10% in Nilotinib 300 mg twice daily or imatinib 400 mg once daily groups) 60-Month Analysisa

 |  | Patients With Newly Diagnosed Ph+ CML-CP
 |  | Nilotinib 300 mg twice daily | Imatinib 400 mg once daily | Nilotinib 300 mg twice daily | Imatinib 400 mg once daily
 |  | N = 279 | N = 280 | N = 279 | N = 280
Body System and Adverse Reaction |  | All Grades (%) |  | CTC Gradesb 3/4 (%)
Skin and subcutaneous tissue disorders | Rash | 38 | 19 | < 1 | 2
 | Pruritus | 21 | 7 | < 1 | 0
 | Alopecia | 13 | 7 | 0 | 0
 | Dry skin | 12 | 6 | 0 | 0
Gastrointestinal disorders | Nausea | 22 | 41 | 2 | 2
 | Constipation | 20 | 8 | < 1 | 0
 | Diarrhea | 19 | 46 | 1 | 4
 | Vomiting | 15 | 27 | < 1 | < 1
 | Abdominal pain upper | 18 | 14 | 1 | < 1
 | Abdominal pain | 15 | 12 | 2 | 0
 | Dyspepsia | 10 | 12 | 0 | 0
Nervous system disorders | Headache | 32 | 23 | 3 | < 1
 | Dizziness | 12 | 11 | < 1 | < 1
General disorders and administration-site conditions | Fatigue | 23 | 20 | 1 | 1
 | Pyrexia | 14 | 13 | < 1 | 0
 | Asthenia | 14 | 12 | < 1 | 0
 | Peripheral edema | 9 | 20 | < 1 | 0
 | Face edema | < 1 | 14 | 0 | < 1
Musculoskeletal and connective tissue disorders | Myalgia | 19 | 19 | < 1 | < 1
 | Arthralgia | 22 | 17 | < 1 | < 1
 | Muscle spasms | 12 | 34 | 0 | 1
 | Pain in extremity | 15 | 16 | < 1 | < 1
 | Back pain | 19 | 17 | 1 | 1
Respiratory, thoracic, and mediastinal disorders | Cough | 17 | 13 | 0 | 0
 | Oropharyngeal pain | 12 | 6 | 0 | 0
 | Dyspnea | 11 | 6 | 2 | < 1
Infections and infestations | Nasopharyngitis | 27 | 21 | 0 | 0
 | Upper respiratory tract infection | 17 | 14 | < 1 | 0
 | Influenza | 13 | 9 | 0 | 0
 | Gastroenteritis | 7 | 10 | 0 | < 1
Eye disorders | Eyelid edema | 1 | 19 | 0 | < 1
 | Periorbital edema | < 1 | 15 | 0 | 0
Psychiatric disorders | Insomnia | 11 | 9 | 0 | 0
Vascular disorder | Hypertension | 10 | 4 | 1 | < 1

Abbreviations: CML-CP, chronic myeloid leukemia-chronic phase; Ph+, Philadelphia chromosome positive.

a Excluding laboratory abnormalities.

b NCI Common Terminology Criteria (CTC) for Adverse Events, version 3.0.

Table 8: Most Frequently Reported Non-Hematologic Adverse Reactions in Adult Patients With Resistant or Intolerant Ph+ CML Receiving Nilotinib 400 mg Twice Daily (regardless of relationship to study drug) (greater than or equal to 10% in any group) 24-Month Analysisa

Body System and Adverse Reaction |  | CML-CP |  | CML-AP
Body System and Adverse Reaction |  | N = 321 |  | N = 137
Body System and Adverse Reaction |  | All Grades (%) | CTC Gradesb 3/4 (%) | All Grades (%) | CTC Gradesb 3/4 (%)
Skin and subcutaneous tissue disorders | Rash | 36 | 2 | 29 | 0
 | Pruritus | 32 | < 1 | 20 | 0
 | Night sweat | 12 | < 1 | 27 | 0
 | Alopecia | 11 | 0 | 12 | 0
Gastrointestinal disorders | Nausea | 37 | 1 | 22 | < 1
 | Constipation | 26 | < 1 | 19 | 0
 | Diarrhea | 28 | 3 | 24 | 2
 | Vomiting | 29 | < 1 | 13 | 0
 | Abdominal pain | 15 | 2 | 16 | 3
 | Abdominal pain upper | 14 | < 1 | 12 | < 1
 | Dyspepsia | 10 | < 1 | 4 | 0
Nervous system disorders | Headache | 35 | 2 | 20 | 1
General disorders and administration-site conditions | Fatigue | 32 | 3 | 23 | < 1
 | Pyrexia | 22 | < 1 | 28 | 2
 | Asthenia | 16 | 0 | 14 | 1
 | Peripheral edema | 15 | < 1 | 12 | 0
Musculoskeletal and connective tissue disorders | Myalgia | 19 | 2 | 16 | < 1
 | Arthralgia | 26 | 2 | 16 | 0
 | Muscle spasms | 13 | < 1 | 15 | 0
 | Bone pain | 14 | < 1 | 15 | 2
 | Pain in extremity | 20 | 2 | 18 | 1
 | Back pain | 17 | 2 | 15 | < 1
 | Musculoskeletal pain | 11 | < 1 | 12 | 1
Respiratory, thoracic, and mediastinal disorders | Cough | 27 | < 1 | 18 | 0
 | Dyspnea | 15 | 2 | 9 | 2
 | Oropharyngeal pain | 11 | 0 | 7 | 0
Infections and infestations | Nasopharyngitis | 24 | < 1 | 15 | 0
 | Upper respiratory tract infection | 12 | 0 | 10 | 0
Metabolism and nutrition disorders | Decreased appetitec | 15 | < 1 | 17 | < 1
Psychiatric disorders | Insomnia | 12 | 1 | 7 | 0
Vascular disorders | Hypertension | 10 | 2 | 11 | < 1

Abbreviations: CML-AP, chronic myeloid leukemia-accelerated phase; CML-CP, chronic myeloid leukemia-chronic phase; Ph+, Philadelphia chromosome positive.

a Excluding laboratory abnormalities.

b NCI Common Terminology Criteria for Adverse Events, version 3.0.

c Also includes preferred term anorexia.

Laboratory Abnormalities

Table 9 shows the percentage of adult patients experiencing treatment-emergent Grade 3/4 laboratory abnormalities in patients who received at least one dose of nilotinib.

Table 9: Percent Incidence of Clinically Relevant Grade 3/4* Laboratory Abnormalities

 | Patient population
 | Newly diagnosed adult Ph+ CML-CP |  | Resistant or intolerant adult Ph+
 | Newly diagnosed adult Ph+ CML-CP |  | CML-CP | CML-AP
 | nilotinib 300 mg twice daily N = 279(%) | imatinib 400 mg once daily N = 280 (%) | nilotinib 400 mg twice daily N = 321(%) | nilotinib 400 mg twice daily N = 137(%)
Hematologic parameters
Thrombocytopenia | 10 | 9 | 30^1 | 42^3
Neutropenia | 12 | 22 | 31^2 | 42^4
Anemia | 4 | 6 | 11 | 27
Biochemistry parameters
Elevated lipase | 9 | 4 | 18 | 18
Hyperglycemia | 7 | < 1 | 12 | 6
Hypophosphatemia | 8 | 10 | 17 | 15
Elevated bilirubin (total) | 4 | < 1 | 7 | 9
Elevated SGPT (ALT) | 4 | 3 | 4 | 4
Hyperkalemia | 2 | 1 | 6 | 4
Hyponatremia | 1 | < 1 | 7 | 7
Hypokalemia | < 1 | 2 | 2 | 9
Elevated SGOT (AST) | 1 | 1 | 3 | 2
Decreased albumin | 0 | < 1 | 4 | 3
Hypocalcemia | < 1 | < 1 | 2 | 5
Elevated alkaline phosphatase | 0 | < 1 | < 1 | 1
Elevated creatinine | 0 | < 1 | < 1 | < 1

Abbreviations: ALT alanine aminotransferase; AST, aspartate aminotransferase; CML-AP, chronic myeloid leukemia-accelerated phase; CML-CP, chronic myeloid leukemia-chronic phase; Ph+, Philadelphia chromosome positive.

*NCI Common Terminology Criteria for Adverse Events, version 3.0.

^1CML-CP: Thrombocytopenia: 12% were Grade 3, 18% were Grade 4.

^2CML-CP: Neutropenia: 16% were Grade 3, 15% were Grade 4.

^3CML-AP: Thrombocytopenia: 11% were Grade 3, 32% were Grade 4.

^4CML-AP: Neutropenia: 16% were Grade 3, 26% were Grade 4.

Elevated total cholesterol (all Grades) occurred in 28% (nilotinib 300 mg twice daily) and 4% (imatinib). Elevated triglycerides (all Grades) occurred in 12% and 8% of patients in the nilotinib and imatinib arms, respectively. Hyperglycemia (all Grades) occurred in 50% and 31% of patients in the nilotinib and imatinib arms, respectively.

Most common biochemistry laboratory abnormalities (all Grades) were alanine aminotransferase increased (72%), blood bilirubin increased (59%), aspartate aminotransferase increased (47%), lipase increased (28%), blood glucose increased (50%), blood cholesterol increased (28%), and blood triglyceride increased (12%).

Treatment Discontinuation in Patients With Ph+ CML-CP Who Have Achieved a Sustained Molecular Response (MR4.5)

In eligible patients who discontinued nilotinib therapy after attaining a sustained molecular response (MR4.5), musculoskeletal symptoms (e.g., myalgia, pain in extremity, arthralgia, bone pain, spinal pain, or musculoskeletal pain), were reported more frequently than before treatment discontinuation in the first year, as noted in Table 10. The rate of new musculoskeletal symptoms generally decreased in the second year after treatment discontinuation.

In the newly diagnosed population in whom musculoskeletal symptoms occurred at any time during the TFR phase, 23/53 (43%) had not resolved by the TFR end date or data cut-off date. In the population previously treated with imatinib in whom musculoskeletal events occurred at any time during the TFR phase, 32/57 (56%) had not resolved by the data cut-off date.

The rate of musculoskeletal symptoms decreased in patients who entered the nilotinib treatment reinitiation (NTRI) phase, at 11/88 (13%) in the newly diagnosed population and 14/56 (25%) in the population previously treated with imatinib. Other adverse reactions observed in the nilotinib re-treatment phase were similar to those observed during nilotinib use in patients with newly diagnosed Ph+ CML-CP and resistant or intolerant Ph+ CML-CP and CML-AP.

Table 10: Musculoskeletal Symptoms Occurring Upon Treatment Discontinuation in the Context of Treatment-Free Remission (TFR)

 | Entire TFR period in all TFR patients |  |  |  | By time interval, in subset of patients in TFR greater than 48 weeks
Ph+ CML-; CP patients | N | Median follow-up in; TFR | Patients with musculoskeletal symptoms |  | N | Year prior to; nilotinib discontinuation |  | 1st year after nilotinib discontinuation |  | 2nd year after; nilotinib discontinuation
Ph+ CML-; CP patients | N | Median follow-up in; TFR | All Grades | Grade 3/4 | N | All Grades | Grade 3/4 | All Grades | Grade 3/4 | All Grades | Grade 3/4
Newly Diagnosed | 190 | 76 weeks | 28% | 1% | 100 | 17% | 0% | 34% | 2% | 9% | 0%
Previously treated with imatinib | 126 | 99 weeks | 45% | 2% | 73 | 14% | 0% | 48% | 3% | 15% | 1%

Abbreviations: CML-CP, chronic myeloid leukemia-chronic phase; Ph+, Philadelphia chromosome positive; TFR, treatment-free remission.

Additional Data From Clinical Trials

The following adverse drug reactions were reported in adult patients in the nilotinib clinical studies at the recommended doses. These adverse drug reactions are ranked under a heading of frequency, the most frequent first using the following convention: common (greater than or equal to 1% and less than 10%), uncommon (greater than or equal to 0.1% and less than 1%), and unknown frequency (single events). For laboratory abnormalities, very common events (greater than or equal to 10%), which were not included in Tables 7 and 8, are also reported. These adverse reactions are included based on clinical relevance and ranked in order of decreasing seriousness within each category, obtained from 2 clinical studies:

1. Adult patients with newly diagnosed Ph+ CML-CP 60 month analysis and,
2. Adult patients with resistant or intolerant Ph+ CML-CP and CMP-AP 24 months’ analysis.

Infections and Infestations: Common: folliculitis. Uncommon: pneumonia, bronchitis, urinary tract infection, candidiasis (including oral candidiasis). Unknown frequency: hepatitis B reactivation, sepsis, subcutaneous abscess, anal abscess, furuncle, tinea pedis.

Neoplasms Benign, Malignant, and Unspecified: Common: skin papilloma. Unknown frequency: oral papilloma, paraproteinemia.

Blood and Lymphatic System Disorders: Common: leukopenia, eosinophilia, febrile neutropenia, pancytopenia, lymphopenia. Unknown frequency: thrombocythemia, leukocytosis.

Immune System Disorders: Unknown frequency: hypersensitivity.

Endocrine Disorders: Uncommon: hyperthyroidism, hypothyroidism. Unknown frequency: hyperparathyroidism secondary, thyroiditis.

Metabolism and Nutrition Disorders: Very Common: hypophosphatemia. Common: electrolyte imbalance (including hypomagnesemia, hyperkalemia, hypokalemia, hyponatremia, hypocalcemia, hypercalcemia, hyperphosphatemia), diabetes mellitus, hyperglycemia, hypercholesterolemia, hyperlipidemia, hypertriglyceridemia. Uncommon: gout, dehydration, increased appetite. Unknown frequency: hyperuricemia, hypoglycemia.

Psychiatric Disorders: Common: depression, anxiety. Unknown frequency: disorientation, confusional state, amnesia, dysphoria.

Nervous System Disorders: Common: peripheral neuropathy, hypoesthesia, paresthesia. Uncommon: intracranial hemorrhage, ischemic stroke, transient ischemic attack, cerebral infarction, migraine, loss of consciousness (including syncope), tremor, disturbance in attention, hyperesthesia, facial paralysis. Unknown frequency: basilar artery stenosis, brain edema, optic neuritis, lethargy, dysesthesia, restless legs syndrome.

Eye Disorders: Common: eye hemorrhage, eye pruritus, conjunctivitis, dry eye (including xerophthalmia). Uncommon: vision impairment, vision blurred, visual acuity reduced, photopsia, hyperemia (scleral, conjunctival, ocular), eye irritation, conjunctival hemorrhage. Unknown frequency: papilledema, diplopia, photophobia, eye swelling, blepharitis, eye pain, chorioretinopathy, conjunctivitis allergic, ocular surface disease.

Ear and Labyrinth Disorders: Common: vertigo. Unknown frequency: hearing impaired, ear pain, tinnitus.

Cardiac Disorders: Common: angina pectoris, arrhythmia (including atrioventricular block, cardiac flutter, extrasystoles, atrial fibrillation, tachycardia, bradycardia), palpitations, electrocardiogram QT prolonged. Uncommon: cardiac failure, myocardial infarction, coronary artery disease, cardiac murmur, coronary artery stenosis, myocardial ischemia, pericardial effusion, cyanosis. Unknown frequency: ventricular dysfunction, pericarditis, ejection fraction decrease.

Vascular Disorders: Common: flushing. Uncommon: hypertensive crisis, peripheral arterial occlusive disease, intermittent claudication, arterial stenosis limb, hematoma, arteriosclerosis. Unknown frequency: shock hemorrhagic, hypotension, thrombosis, peripheral artery stenosis.

Respiratory, Thoracic and Mediastinal Disorders: Common: dyspnea exertional, epistaxis, dysphonia. Uncommon: pulmonary edema, pleural effusion, interstitial lung disease, pleuritic pain, pleurisy, pharyngolaryngeal pain, throat irritation. Unknown frequency: pulmonary hypertension, wheezing.

Gastrointestinal Disorders: Common: pancreatitis, abdominal discomfort, abdominal distension, dysgeusia, flatulence. Uncommon: gastrointestinal hemorrhage, melena, mouth ulceration, gastroesophageal reflux, stomatitis, esophageal pain, dry mouth, gastritis, sensitivity of teeth. Unknown frequency: gastrointestinal ulcer perforation, retroperitoneal hemorrhage, hematemesis, gastric ulcer, esophagitis ulcerative, subileus, enterocolitis, hemorrhoids, hiatus hernia, rectal hemorrhage, gingivitis.

Hepatobiliary Disorders: Very common: hyperbilirubinemia. Common: hepatic function abnormal. Uncommon: hepatotoxicity, toxic hepatitis, jaundice. Unknown frequency: cholestasis, hepatomegaly.

Skin and Subcutaneous Tissue Disorders: Common: eczema, urticaria, erythema, hyperhidrosis, contusion, acne, dermatitis (including allergic, exfoliative and acneiform). Uncommon: exfoliative rash, drug eruption, pain of skin, ecchymosis. Unknown frequency: psoriasis, erythema multiforme, erythema nodosum, skin ulcer, palmar-plantar erythrodysesthesia syndrome, petechiae, photosensitivity, blister, dermal cyst, sebaceous hyperplasia, skin atrophy, skin discoloration, skin exfoliation, skin hyperpigmentation, skin hypertrophy, hyperkeratosis.

Musculoskeletal and Connective Tissue Disorders: Common: bone pain, musculoskeletal chest pain, musculoskeletal pain, back pain, neck pain, flank pain, muscular weakness. Uncommon: musculoskeletal stiffness, joint swelling. Unknown frequency: arthritis.

Renal and Urinary Disorders: Common: pollakiuria. Uncommon: dysuria, micturition urgency, nocturia. Unknown frequency: renal failure, hematuria, urinary incontinence, chromaturia.

Reproductive System and Breast Disorders: Uncommon: breast pain, gynecomastia, erectile dysfunction. Unknown frequency: breast induration, menorrhagia, nipple swelling.

General Disorders and Administration Site Conditions: Common: pyrexia, chest pain (including non-cardiac chest pain), pain, chest discomfort, malaise. Uncommon: gravitational edema, influenza-like illness, chills, feeling body temperature change (including feeling hot, feeling cold). Unknown frequency: localized edema.

Investigations: Very Common: alanine aminotransferase increased, aspartate aminotransferase increased, lipase increased, lipoprotein cholesterol (including very low density and high density) increased, total cholesterol increased, blood triglycerides increased. Common: hemoglobin decreased, blood amylase increased, gamma-glutamyltransferase increased, blood creatinine phosphokinase increased, blood alkaline phosphatase increased, weight decreased, weight increased, globulins decreased. Uncommon: blood lactate dehydrogenase increased, blood urea increased. Unknown frequency: troponin increased, blood bilirubin unconjugated increased, insulin C-peptide decreased, blood parathyroid hormone increased.

In Pediatric Patients With Newly Diagnosed Ph+ CML-CP or Resistant or Intolerant Ph+ CML-CP

In pediatric patients with Ph+ CML-CP, the most common (greater than 20%) non-hematologic adverse reactions were hyperbilirubinemia, headache, alanine aminotransferase increased, rash, pyrexia, nausea, aspartate aminotransferase increased, pain in extremity, upper respiratory tract infection, vomiting, diarrhea, and nasopharyngitis. The most common (greater than 5%) Grade 3/4 non-hematologic adverse reactions were hyperbilirubinemia, rash, alanine aminotransferase increased, and neutropenia.

Laboratory abnormalities of hyperbilirubinemia (Grade 3/4: 16%) and transaminase elevation (AST Grade 3/4: 2.9%, ALT Grade 3/4: 10%), were reported at a higher frequency than in adult patients.

The most common hematological laboratory abnormalities (greater than or equal to 30% of patients, of all Grades) were decreases in total white blood cells (54%), platelet count (44%), absolute neutrophils (44%), hemoglobin (38%), and absolute lymphocytes (36%).

Discontinuation of study treatment due to adverse reactions occurred in 15 patients (22%). The most frequent adverse reactions leading to discontinuation were hyperbilirubinemia (9%) and rash (6%).

Increase in QTcF greater than 30 msec from baseline was observed in 19 patients (28%). No patient had an absolute QTcF of greater than 500 msec or QTcF increase of greater than 60 msec from baseline.

Growth Retardation in Pediatric Population

Close monitoring of growth in pediatric patients under nilotinib treatment is recommended [see Warnings and Precautions (5.14)].

Additional pediatric use information is approved for Novartis Pharmaceuticals Corporation’s Tasigna® (nilotinib) capsules. However, due to Novartis Pharmaceuticals Corporation’s marketing exclusivity rights, this drug product is not labeled with that pediatric information.

6.2 Postmarketing Experience

The following adverse reactions have been identified during postapproval use of nilotinib. Because these reactions are reported voluntarily from a population of uncertain size, it is not always possible to reliably estimate their frequency or establish a causal relationship to drug exposure.

Blood and Lymphatic System Disorders: thrombotic microangiopathy

Nervous System Disorders: facial paralysis

Musculoskeletal and Connective Tissue Disorders: osteonecrosis

7 DRUG INTERACTIONS

7.1 Effect of Other Drugs on Nilotinib Capsules

Strong CYP3A Inhibitors

Avoid concomitant use of strong CYP3A inhibitors with Nilotinib Capsules. If concomitant use cannot be avoided, reduce Nilotinib Capsules dose [see Dosage and Administration (2.8)].

Nilotinib is a CYP3A substrate [see Clinical Pharmacology (12.3)]. Concomitant use with a strong CYP3A inhibitor increases nilotinib exposure [see Clinical Pharmacology (12.3)], which may increase the risk of Nilotinib Capsules adverse reactions.

Strong CYP3A Inducers

Avoid concomitant use of strong CYP3A inducers with Nilotinib Capsules.

Nilotinib is a CYP3A substrate [see Clinical Pharmacology (12.3)]. Concomitant use with a strong CYP3A inducer decreases nilotinib exposure [see Clinical Pharmacology (12.3)], which may reduce Nilotinib Capsules efficacy.

Proton Pump Inhibitors

Avoid concomitant use of proton pump inhibitors (PPI) with Nilotinib Capsules. As an alternative to PPIs, use H2 blockers approximately 10 hours before or approximately 2 hours after the dose of Nilotinib Capsules, or use antacids approximately 2 hours before or approximately 2 hours after the dose of Nilotinib Capsules.

Nilotinib displays pH-dependent aqueous solubility [see Description (11)]. Concomitant use with a PPI decreases nilotinib concentrations [see Clinical Pharmacology (12.3)], which may reduce Nilotinib Capsules efficacy.

7.2 Drugs That Prolong the QT Interval

Avoid coadministration of Nilotinib Capsules with agents that may prolong the QT interval, such as anti-arrhythmic drugs [see Boxed Warning, Dosage and Administration (2.4), Warnings and Precautions (5.2), Drug Interactions (7.1), Clinical Pharmacology (12.2)].

Nilotinib is associated with a clinically significant concentration-dependent QT prolongation [see Clinical Pharmacology (12.2)].

8 USE IN SPECIFIC POPULATIONS

8.1 Pregnancy

Risk Summary

Based on findings from animal studies and the mechanism of action, Nilotinib Capsules can cause fetal harm when administered to a pregnant woman [see Clinical Pharmacology (12.1)]. There are no available data in pregnant women to inform the drug-associated risk. In animal reproduction studies, administration of nilotinib to pregnant rats and rabbits during organogenesis caused adverse developmental outcomes, including embryo-fetal lethality, fetal effects, and fetal variations in rats and rabbits at maternal exposures (AUC) approximately 2 and 0.5 times, respectively, the exposures in patients at the recommended dose (see Data). Advise pregnant women of the potential risk to a fetus.

The background risk of major birth defects and miscarriage for the indicated population is unknown. All pregnancies have a background risk of birth defect, loss, or other adverse outcomes. In the U.S. general population, the estimated background risk of major birth defects and miscarriage in clinically recognized pregnancies are 2% to 4% and 15% to 20%, respectively.

Data

Animal Data

In embryo-fetal development studies in rats and rabbits, pregnant animals received oral doses of nilotinib up to 100 mg/kg/day and 300 mg/kg/day, respectively, during the period of organogenesis.

In rats, oral administration of nilotinib produced embryo-lethality/fetal effects at doses ≥ 30 mg/kg/day. At ≥ 30 mg/kg/day, skeletal variations of incomplete ossification of the frontals and misshapen sternebra were noted, and there was an increased incidence of small renal papilla and fetal edema. At 100 mg/kg/day, nilotinib was associated with maternal toxicity (decreased gestation weight, gravid uterine weight, net weight gain, and food consumption) and resulted in a single incidence of cleft palate and two incidences of pale skin were noted in the fetuses. A single incidence of dilated ureters was noted in a fetus also displaying small renal papilla at 100 mg/kg/day. Additional variations of forepaw and hindpaw phalanx unossified, fused sternebra, bipartite sternebra ossification, and incomplete ossification of the cervical vertebra were noted at 100 mg/kg/day.

In rabbits, oral administration of nilotinib resulted in the early sacrifice of two females, maternal toxicity and increased resorption of fetuses at 300 mg/kg/day. Fetal skeletal variations (incomplete ossification of the hyoid, bent hyoid, supernumerary short detached ribs and the presence of additional ossification sites near the nasals, frontals and in the sternebral column) were also increased at this dose in the presence of maternal toxicity. Slight maternal toxicity was evident at 100 mg/kg/day but there were no reproductive or embryo-fetal effects at this dose.

At 30 mg/kg/day in rats and 300 mg/kg/day in rabbits, the maternal systemic exposure (AUC) were 72700 ng*hr/mL and 17100 ng*hr/mL, respectively, representing approximately 2 and 0.5 times the exposure in humans at the highest recommended dose 400 mg twice daily.

When pregnant rats were dosed with nilotinib during organogenesis and through lactation, the adverse effects included a longer gestational period, lower pup body weights until weaning and decreased fertility indices in the pups when they reached maturity, all at a maternal dose of 60 mg/kg (i.e., 360 mg/m^2, approximately 0.7 times the clinical dose of 400 mg twice daily based on body surface area). At doses up to 20 mg/kg (i.e., 120 mg/m^2, approximately 0.25 times the clinical dose of 400 mg twice daily based on body surface area) no adverse effects were seen in the maternal animals or the pups.

8.2 Lactation

Risk Summary

There are no data on the presence of nilotinib or its metabolites in human milk or its effects on a breastfed child or on milk production. However, nilotinib is present in the milk of lactating rats. Because of the potential for serious adverse reactions in a breastfed child, advise women not to breastfeed during treatment with Nilotinib Capsules and for 14 days after the last dose.

Animal Data

After a single 20 mg/kg of [^14C] nilotinib dose to lactating rats, the transfer of parent drug and its metabolites into milk was observed. The overall milk-to-plasma exposure ratio of total radioactivity was approximately 2, based on the AUC0-24h or AUC0-INF values. No rat metabolites of nilotinib were detected that were unique to milk.

8.3 Females and Males of Reproductive Potential

Based on animal studies, Nilotinib Capsules can cause fetal harm when administered to a pregnant woman [see Use in Specific Populations (8.1)].

Pregnancy Testing

Females of reproductive potential should have a pregnancy test prior to starting treatment with Nilotinib Capsules.

Contraception

Females

Advise females of reproductive potential to use effective contraception during treatment with Nilotinib Capsules and for 14 days after the last dose.

Infertility

The risk of infertility in females or males of reproductive potential has not been studied in humans. In studies in rats and rabbits, the fertility in males and females was not affected [see Nonclinical Toxicology (13.1)].

8.4 Pediatric Use

The frequency, type, and severity of adverse reactions observed were generally consistent with those observed in adults, with the exception of the laboratory abnormalities of hyperbilirubinemia (Grade 3/4: 16%) and transaminase elevation (AST Grade 3/4: 2.9%, ALT Grade 3/4: 10%), which were reported at a higher frequency in pediatric patients than in adults [see Adverse Reactions (6.1)]. For pediatric growth and development, growth retardation has been reported in pediatric patients with Ph+ CML-CP treated with nilotinib [see Warnings and Precautions (5.14 and 5.12), Adverse Reactions (6.1)].

The safety and effectiveness of nilotinib in pediatric patients below the age of 1 year with newly diagnosed, or resistant or intolerant Ph+ CML in chronic phase and accelerated phase, have not been established.

Additional pediatric use information is approved for Novartis Pharmaceuticals Corporation’s Tasigna® (nilotinib) capsules. However, due to Novartis Pharmaceuticals Corporation’s marketing exclusivity rights, this drug product is not labeled with that pediatric information.

8.5 Geriatric Use

In the clinical trials of nilotinib (patients with newly diagnosed Ph+ CML-CP and resistant or intolerant Ph+ CML-CP and CML-AP), approximately 12% and 30% of patients were 65 years or over, respectively.

- Patients with newly diagnosed Ph+ CML-CP: There was no difference in major molecular response between patients aged less than 65 years and those greater than or equal to 65 years.
- Patients with resistant or intolerant CML-CP: There was no difference in major cytogenetic response rate between patients aged less than 65 years and those greater than or equal to 65 years.
- Patients with resistant or intolerant CML-AP: The hematologic response rate was 44% in patients less than 65 years of age and 29% in patients greater than or equal to 65 years.

No major differences for safety were observed in patients greater than or equal to 65 years of age as compared to patients less than 65 years.

8.6 Cardiac Disorders

In the clinical trials, patients with a history of uncontrolled or significant cardiovascular disease, including recent myocardial infarction, congestive heart failure, unstable angina or clinically significant bradycardia, were excluded. Caution should be exercised in patients with relevant cardiac disorders [see Boxed Warning, Warnings and Precautions (5.2)].

8.7 Hepatic Impairment

Reduce the Nilotinib Capsules dosage in patients with hepatic impairment and monitor the QT interval closely [see Dosage and Administration (2.7), Clinical Pharmacology (12.3)].

10 OVERDOSAGE

Overdose with nilotinib has been reported, where an unspecified number of nilotinib were ingested in combination with alcohol and other drugs. Events included neutropenia, vomiting, and drowsiness. In the event of overdose, observe the patient and provide appropriate supportive treatment.

11 DESCRIPTION

Nilotinib Capsules contains nilotinib d-tartrate, which belongs to a pharmacologic class of drugs known as kinase inhibitors.

Nilotinib d-tartrate is a white to yellow powder with the molecular formula and weight, respectively, of C32H28F3N7O7 and 679.61 g/mol (corresponding molecular formula and weight of nilotinib base, anhydrous are C28H22F3N7O and 529 g/mol, respectively). The solubility of nilotinib d-tartrate in aqueous solutions decreases with increasing pH. The pKa1 of nilotinib d-tartrate was determined to be 4.0.

The chemical name of nilotinib d-tartrate is 4-methyl-N-[3-(4-methyl-1H-imidazol-1-yl)-5-(trifluoromethyl)phenyl]-3-((4-(pyridin-3-yl)pyrimidin-2-yl)amino)benzamide D-Tartrate. Its structure is shown below:

Nilotinib Capsules, for oral use, contain 50 mg, 150 mg, or 200 mg nilotinib, anhydrous (equivalent to 64.172 mg, 192.517 mg, and 256.689 mg nilotinib d-tartrate, respectively). The inactive ingredients of Nilotinib Capsules are colloidal silicon dioxide, crospovidone, lactose monohydrate, magnesium aluminometasilicate, magnesium stearate, and polysorbate 80. The inactive ingredients in the empty capsules contain gelatin, iron oxide (black), iron oxide (red), iron oxide (yellow), and titanium dioxide. The black ink contains iron oxide (black), potassium hydroxide, propylene glycol, shellac, and strong ammonia solution.

12 CLINICAL PHARMACOLOGY

12.1 Mechanism of Action

Nilotinib is an inhibitor of the BCR-ABL kinase. Nilotinib binds to and stabilizes the inactive conformation of the kinase domain of ABL protein. In vitro, nilotinib inhibited BCR-ABL mediated proliferation of murine leukemic cell lines and human cell lines derived from patients with Ph+ CML. Under the conditions of the assays, nilotinib was able to overcome imatinib resistance resulting from BCR-ABL kinase mutations, in 32 out of 33 mutations tested. Nilotinib inhibited the autophosphorylation of the following kinases at IC50 values as indicated: BCR-ABL (20 to 60 nM), PDGFR (69 nM), c-KIT (210 nM), CSF-1R (125 to 250 nM), and DDR1 (3.7 nM).

12.2 Pharmacodynamics

A relationship between nilotinib exposure and a greater likelihood of response and safety events, including a higher occurrence of total bilirubin elevations, was observed in clinical studies.

Nilotinib time course of pharmacodynamic response is unknown.

Cardiac Electrophysiology

Nilotinib is associated with concentration-dependent QT prolongation. At a dose of Nilotinib Capsules 400 mg twice daily given without food in healthy subjects, the maximum mean placebo-adjusted QTcF changes were 10.4 msec (90% CI: 2.85, 18.0). After a single dose of Nilotinib Capsules 800 mg (two times the maximum approved recommended dosage) given with a high fat meal to healthy subjects, the maximum mean placebo-adjusted QTcF changes were 18.0 msec (90% CI: 9.65, 25.8). Peak plasma concentrations in the QT study were 26% lower than or comparable with those observed in patients enrolled in the single-arm study [see Boxed Warning, Warnings and Precautions (5.2), Adverse Reactions (6.1)].

12.3 Pharmacokinetics

Nilotinib single-dose maximum concentration (Cmax) and area under the time concentration curve (AUC) in fasted healthy subjects receiving Nilotinib Capsules are presented in Table 11.

Table 11: Nilotinib Geometric Mean (%CV) Single-Dose Exposure

Nilotinib Capsules Dose | Cmax (ng/mL) | AUC0-inf (ng•hr/mL)
200 mg (0.5 times the maximum approved recommended dose) | 615 (38%) | 10620 (45%)
50 mg (0.25 times the maximum approved recommended dose) | 303 (29%) | 4550 (48%)

Steady-state nilotinib exposure was dose-dependent with less than dose-proportional increases in systemic exposure at dose levels higher than 400 mg given as once or twice daily dosing. In adult patients with resistant or intolerant Ph+ CML given nilotinib 400 mg twice daily, the steady-state mean (% CV) Cmax and AUC0-12h were 2260 ng/mL (35%) and 18000 ng∙h/mL (33%), respectively. In adult patients with newly diagnosed Ph+ CML given nilotinib 300 mg twice daily, the steady-state mean (% CV) Cmax and AUC0-12h were 1540 ng/mL (48%) and 13337 ng∙h/mL (46%), respectively.

Steady state conditions were achieved by Day 8. An increase in serum exposure to nilotinib between the first dose and steady state was approximately 2-fold for daily dosing and 3.8-fold for twice daily dosing. The average steady state nilotinib trough and peak concentrations did not change over 12 months.

Absorption

The median time (range) to reach peak plasma nilotinib concentrations (Tmax) is 3.3 hours (1.0 to 5.5) following single dose administration of Nilotinib Capsules 200 mg (0.5 times the maximum approved recommended dose) in fasted healthy subjects.

Median steady-state trough concentration of nilotinib was decreased by 53% in patients with total gastrectomy compared to patients who had not undergone surgeries [see Warnings and Precautions (5.10)].

Effect of Food

Nilotinib AUC increased by 68% with a high-fat meal (approximately 800 to 1000 calories, 50% fat) and increased by 53% with a low-fat meal (approximately 400 to 500 calories, 25% fat) compared to the fasted state following a single dose of Nilotinib Capsules 200 mg (0.5 times the maximum approved recommended dose) in healthy subjects.

Distribution

Serum protein binding is approximately 98% with a blood-to-serum ratio of 0.68.

Elimination

The mean (CV%) elimination half-life of nilotinib is 10 hours (30%) following a single dose of Nilotinib Capsules 200 mg (0.5 times the maximum approved recommended dose) in fasted healthy subjects.

The mean (CV%) apparent elimination half-life is estimated to be approximately 17 hours (69%) and the mean (CV%) apparent clearance approximates 29 L/h (61%) in patients.

Metabolism

Nilotinib is primarily metabolized via CYP3A4-mediated oxidation and to a minor extent by CYP2C8.

Excretion

After a single dose of radiolabeled nilotinib, more than 90% of the administered dose was eliminated within 7 days: 93% of the dose in feces. Parent drug accounted for 69% of the dose.

Specific Populations

No clinically significant differences in the pharmacokinetics of nilotinib were observed based on age, sex, race/ethnicity, or body weight. The effect of renal impairment on nilotinib pharmacokinetics is unknown.

Additional pediatric use information is approved for Novartis Pharmaceuticals Corporation’s Tasigna® (nilotinib) capsules. However, due to Novartis Pharmaceuticals Corporation’s marketing exclusivity rights, this drug product is not labeled with that pediatric information.

Patients with Hepatic Impairment

Nilotinib mean AUC increased 1.4-fold in mild (Child-Pugh class A), 1.4-fold in moderate (Child-Pugh class B), and 1.6-fold in severe (Child-Pugh class C) hepatic impairment subjects following a single dose of Nilotinib Capsules 200 mg (0.5 times the maximum approved recommended dose).

Drug Interaction Studies

Clinical Studies

Strong CYP3A Inhibitors: Nilotinib AUC increased by approximately 3-fold following concomitant administration of ketoconazole (strong CYP3A inhibitor) 400 mg once daily for 6 days. Nilotinib AUC increased by 1.3-fold with concomitant use with double-strength grapefruit juice.

Strong CYP3A Inducers: Nilotinib AUC decreased by approximately 80% following concomitant use with rifampicin (strong CYP3A inducer) 600 mg daily.

Proton Pump Inhibitors (PPIs): Nilotinib displays pH-dependent aqueous solubility [see Description (11)]. Nilotinib AUC decreased by 34% following concomitant use of multiple doses of esomeprazole (PPI) 40 mg daily.

Other Drugs: No clinically significant differences in nilotinib pharmacokinetics were observed when used concomitantly with imatinib (moderate CYP3A inhibitor), famotidine (an H2 blocker), or an antacid. No clinically significant differences in the pharmacokinetics of the following drugs were observed when used concomitantly with nilotinib: oral midazolam (CYP3A substrate), imatinib, or warfarin (CYP2C9 substrate).

In Vitro Studies

Cytochrome P450 (CYP) Enzymes: Nilotinib is a competitive inhibitor of CYP2C8, CYP2D6, and is an inducer of CYP2B6 and CYP2C8.

Transporter Systems: Nilotinib is a substrate of P-gp and an inhibitor of UGT1A1 and P-gp.

12.5 Pharmacogenomics

Nilotinib can increase bilirubin levels. The (TA)7/(TA)7 genotype of UGT1A1 was associated with a statistically significant increase in the risk of hyperbilirubinemia relative to the (TA)6/(TA)6 and (TA)6/(TA)7 genotypes. However, the largest increases in bilirubin were observed in the (TA)7/(TA)7 genotype (UGT1A1*28) patients [see Warnings and Precautions (5.6)].

13 NONCLINICAL TOXICOLOGY

13.1 Carcinogenesis, Mutagenesis, Impairment of Fertility

A 2-year carcinogenicity study was conducted orally in rats at nilotinib doses of 5, 15, and 40 mg/kg/day. Exposures in animals at the highest dose tested were approximately 2- to 3-fold the human exposure (based on AUC) at the nilotinib dose of 400 mg twice daily. The study was negative for carcinogenic findings. A 26-week carcinogenicity study was conducted orally in Tg.rasH2 mice, a model genetically modified to enhance susceptibility to neoplastic transformation, at nilotinib doses of 30, 100, and 300 mg/kg/day. Nilotinib induced in the skin and subcutis statistically significant increases in the incidence of papillomas in females and of papillomas and combined papillomas and carcinomas in males at 300 mg/kg/day. The no-observed-adverse- effect-level (NOAEL) for skin neoplastic lesions was 100 mg/kg/day.

Nilotinib was not mutagenic in a bacterial mutagenesis (Ames) assay, was not clastogenic in a chromosome aberration assay in human lymphocytes, did not induce DNA damage (comet assay) in L5178Y mouse lymphoma cells, nor was it clastogenic in an in vivo rat bone marrow micronucleus assay with two oral treatments at doses up to 2000 mg/kg/dose.

There were no effects on male or female rat and female rabbit mating or fertility at doses up to 180 mg/kg in rats (approximately 4- to 7-fold for males and females, respectively, the AUC in patients at the dose of 400 mg twice daily) or 300 mg/kg in rabbits (approximately one-half the AUC in patients at the dose of 400 mg twice daily). The effect of nilotinib on human fertility is unknown. In a study where male and female rats were treated with nilotinib at oral doses of 20 to 180 mg/kg/day (approximately 1- to 6.6-fold the AUC in patients at the dose of 400 mg twice daily) during the pre-mating and mating periods and then mated, and dosing of pregnant rats continued through gestation Day 6, nilotinib increased post-implantation loss and early resorption, and decreased the number of viable fetuses and litter size at all doses tested.

14 CLINICAL STUDIES

14.1 Adult Newly Diagnosed Ph+ CML-CP

The ENESTnd (Evaluating Nilotinib Efficacy and Safety in clinical Trials-Newly Diagnosed patients) study (NCT00471497) was an open-label, multicenter, randomized trial conducted to determine the efficacy of nilotinib versus imatinib tablets in adult patients with cytogenetically confirmed newly diagnosed Ph+ CML-CP. Patients were within 6 months of diagnosis and were previously untreated for CML-CP, except for hydroxyurea and/or anagrelide. Efficacy was based on a total of 846 patients: 283 patients in the imatinib 400 mg once daily group, 282 patients in the nilotinib 300 mg twice daily group, 281 patients in the nilotinib 400 mg twice daily group (an unapproved dosage regimen for this indication).

Median age was 46 years in the imatinib group and 47 years in both nilotinib groups, with 12%, 13%, and 10% of patients greater than or equal to 65 years of age in imatinib 400 mg once daily, nilotinib 300 mg twice daily and nilotinib 400 mg twice daily treatment groups, respectively. There were slightly more male than female patients in all groups (56%, 56%, and 62% in imatinib 400 mg once daily, nilotinib 300 mg twice daily and nilotinib 400 mg twice daily treatment groups, respectively). More than 60% of all patients were White, and 25% were Asian.

The primary data analysis was performed when all 846 patients completed 12 months of treatment (or discontinued earlier). Subsequent analyses were done when patients completed 24, 36, 48, and 60 months of treatment (or discontinued earlier). The median time on treatment was approximately 61 months in all three treatment groups.

The primary efficacy endpoint was major molecular response (MMR) at 12 months after the start of study medication. MMR was defined as less than or equal to 0.1% BCR-ABL/ABL % by international scale measured by RQ-PCR, which corresponds to a greater than or equal to 3 log reduction of BCR-ABL transcript from standardized baseline. Efficacy endpoints are summarized in Table 12.

Two patients in the nilotinib arm progressed to either accelerated phase or blast crisis (both within the first 6 months of treatment) while 12 patients on the imatinib arm progressed to either accelerated phase or blast crisis (7 patients within first 6 months, 2 patients within 6 to 12 months, 2 patients within 12 to 18 months and 1 patient within 18 to 24 months).

Table 12: Efficacy (MMR and CCyR) of Nilotinib Compared to imatinib in Adult Newly Diagnosed Ph+ CML-CP (ENESTnd)

 | Nilotinib 300 mg twice daily |  | Imatinib 400 mg once daily
 | N = 282 |  | N = 283
MMR at 12 months (95% CI) | 44% (38.4, 50.3) |  | 22% (17.6, 27.6)
P-Valuea |  | < 0.0001
CCyRb by 12 months (95% CI) | 80% (75.0, 84.6) |  | 65% (59.2, 70.6)
MMR at 24 months (95% CI) | 62% (55.8, 67.4) |  | 38% (31.8, 43.4)
CCyRb by 24 months (95% CI) | 87% (82.4, 90.6) |  | 77% (71.7, 81.8)

Abbreviation: CI, confidence interval.

a CMH test stratified by Sokal risk group.

b CCyR: 0% Ph+ metaphases. Cytogenetic responses were based on the percentage of Ph+ metaphases among greater than or equal to 20 metaphase cells in each bone marrow sample.

By the 60 months, MMR was achieved by 77% of patients on nilotinib and 60% of patients on imatinib; MR4.5 was achieved by 53.5% of patients on nilotinib and 31.4% on imatinib. Median overall survival was not reached in either arm. At the time of the 60-month final analysis, the estimated survival rate was 93.7% for patients on nilotinib and 91.7% for patients on imatinib.

14.2 Adult Patients With Resistant or Intolerant Ph+ CML-CP and CML-AP

Study CAMN107A2101 (referred to as Study A2101) (NCT00109707) was a single-arm, open-label, multicentre study conducted to evaluate the efficacy and safety of nilotinib (400 mg twice daily) in patients with imatinib-resistant or - intolerant CML with separate cohorts for chronic and accelerated phase disease. The definition of imatinib resistance included failure to achieve a complete hematologic response (by 3 months), cytogenetic response (by 6 months) or major cytogenetic response (by 12 months) or progression of disease after a previous cytogenetic or hematologic response. Imatinib intolerance was defined as discontinuation of treatment due to toxicity and lack of a major cytogenetic response at time of study entry. At the time of data cutoff, 321 patients with CML-CP and 137 patients with CML-AP with a minimum follow-up of 24 months were enrolled. In this study, about 50% of CML-CP and CML-AP patients were males, over 90% (CML-CP) and 80% (CML-AP) were White, and approximately 30% were age 65 years or older.

Overall, 73% of patients were imatinib resistant while 27% were imatinib intolerant. The median time of prior imatinib treatment was approximately 32 (CML-CP) and 28 (CML-AP) months. Prior therapy included hydroxyurea in 85% of patients, interferon in 56% and stem cell or bone marrow transplant in 8%. The median highest prior imatinib dose was 600 mg per day for patients with CML-CP and CML-AP, and the highest prior imatinib dose was greater than or equal to 600 mg/day in 74% of all patients with 40% of patients receiving imatinib doses greater than or equal to 800 mg/day.

Median duration of nilotinib treatment was 18.4 months in patients with CML-CP and 8.7 months in patients with CML-AP.

The efficacy endpoint in CML-CP was unconfirmed major cytogenetic response (MCyR) which included complete and partial cytogenetic responses.

The efficacy endpoint in CML-AP was confirmed hematologic response (HR), defined as either a complete hematologic response (CHR) or no evidence of leukemia (NEL). The rates of response for CML-CP and CMLAP patients are reported in Table 13.

Median durations of response had not been reached at the time of data analysis.

Table 13: Efficacy of Nilotinib in Adult Resistant or Intolerant Ph+ CML-CP and CML-AP (Study A2101)

Cytogenetic response rate (unconfirmed) (%)a
 | Chronic phase (n = 321)
Major (95% CI) | 51% (46%–57%)
Complete (95% CI) | 37% (32%–42%)
Partial (95% CI) | 15% (11%–19%)
 | Accelerated phase (n = 137)
Hematologic response rate (confirmed) (95% CI)b | 39% (31%–48%)
Complete hematologic response rate (95% CI) | 30% (22%–38%)
No evidence of leukemia (95% CI) | 9% (5%–16%)

a Cytogenetic response criteria: Complete (0% Ph+ metaphases) or partial (1% to 35%). Cytogenetic responses were based on the percentage of Ph-positive metaphases among greater than or equal to 20 metaphase cells in each bone marrow sample.

b Hematologic response = CHR + NEL (all responses confirmed after 4 weeks).

CHR (CML-CP): WBC less than 10 x 10^9/L, platelets less than 450,000/mm^3, no blasts or promyelocytes in peripheral blood, less than 5% myelocytes + metamyelocytes in bone marrow, less than 20% basophils in peripheral blood, and no extramedullary involvement. CHR (CML-AP): neutrophils greater than or equal to 1.5 x 10^9/L, platelets greater than or equal to 100 x 10^9/L, no myeloblasts in peripheral blood, myeloblasts less than 5% in bone marrow, and no extramedullary involvement.

NEL: same criteria as for CHR but neutrophils greater than or equal to 1.0 x 10^9/L and platelets greater than or equal to 20 x 10^9/L without transfusions or bleeding.

Adult Patients With Chronic Phase

The MCyR rate in 321 CML-CP patients was 51%. The median time to MCyR among responders was 2.8 months (range, 1 to 28 months). The median duration of MCyR cannot be estimated. The median duration of exposure on this single arm-trial was 18.4 months. Among the CML-CP patients who achieved MCyR, 62% of them had MCyR lasting more than 18 months. The CCyR rate was 37%.

Adult Patients With Accelerated Phase

The overall confirmed hematologic response rate in 137 patients with CML-AP was 39%. The median time to first hematologic response among responders was 1 month (range, 1 to 14 months). Among the CML-AP patients who achieved HR, 44% of them had a response lasting for more than 18 months.

After imatinib failure, 24 different BCR-ABL mutations were noted in 42% of chronic phase and 54% of accelerated phase CML patients who were evaluated for mutations.

14.3 Treatment Discontinuation in Newly Diagnosed Ph+ CML-CP Patients Who Have Achieved a Sustained Molecular Response (MR4.5)

The ENEST freedom (Evaluating Nilotinib Efficacy and Safety in clinical Trials-freedom) study (NCT01784068) is an open-label, multicenter, single-arm study, where 215 adult patients with Ph+ CML-CP treated with nilotinib in first-line for ≥ 2 years who achieved MR4.5 as measured with the MolecularMD MRDx® BCR-ABL Test were enrolled to continue nilotinib treatment for an additional 52 weeks (nilotinib consolidation phase).

Of the 215 patients, 190 patients (88.4%) entered the “Treatment-Free Remission” (TFR) phase after achieving a sustained molecular response (MR4.5) during the consolidation phase, defined by the following criteria:

- The 4 last quarterly assessments (taken every 12 weeks) were at least MR4 (BCR-ABL/ABL ≤ 0.01% IS), and maintained for 1 year
- The last assessment being MR4.5 (BCR-ABL/ABL ≤ 0.0032% IS)
- No more than two assessments falling between MR4 and MR4.5 (0.0032% IS < BCR-ABL/ABL ≤ 0.01% IS).

The median age of patients who entered the TFR phase was 55 years, 49.5% were females, and 21.1% of the patients were ≥ 65 years of age. BCR-ABL levels were monitored every 4 weeks during the first 48 weeks of the TFR phase. Monitoring frequency was intensified to every 2 weeks upon the loss of MR4.0. Biweekly monitoring ended at one of the following time points:

- Loss of MMR requiring patient to reinitiate nilotinib treatment
- When the BCR-ABL levels returned to a range between MR4.0 and MR4.5
- When the BCR-ABL levels remained lower than MMR for 4 consecutive measurements (8 weeks from initial loss of MR4.0).

Any patient with loss of MMR during the TFR phase reinitiated nilotinib treatment at 300 mg twice daily or at a reduced dose level of 400 mg once daily if required from the perspective of tolerance, within 5 weeks after the collection date of the blood sample demonstrating loss of MMR. Patients who required reinitiation of nilotinib treatment were monitored for BCR-ABL levels every 4 weeks for the first 24 weeks and then every 12 weeks thereafter in patients who regained MMR.

Efficacy was based on the 96-week analysis data cut-off date, by which time, 91 patients (47.9%) discontinued from the TFR phase due to loss of MMR, and 1 (0.5%), 1 (0.5%), 1 (0.5%) and 3 patients (1.6%) due to death from unknown cause, physician decision, lost to follow-up and subject decision, respectively. Among the 91 patients who discontinued the TFR phase due to loss of MMR, 88 patients restarted nilotinib treatment and 3 patients permanently discontinued from the study.

By the 96-week data cut-off, of the 88 patients who restarted treatment due to loss of MMR in the TFR phase, 87 patients (98.9%) patients regained MMR (one patient discontinued study permanently due to subject decision after 7.1 weeks of retreatment without regaining MMR) and 81 patients (92.0%) regained MR4.5 by the time of the cut-off date. The cumulative rate of MMR and MR4.5 regained at 24 weeks since treatment reinitiation was 97.7% (86/88 patients) and 86.4% (76/88 patients), respectively.

Table 14: Efficacy Results for ENEST freedom

Patients who entered the treatment free remission (TFR) phase (full analysis set, N = 190)
 | Patients in TFR phase^1 at the specified time point |  | Loss of MMR^2 by the specified time point
 | % | 95% CI | %
24 weeks | 62.1 | (54.8, 69.0) | 35.8
48 weeks | 51.6 | (44.2, 58.9) | 45.8
96 weeks | 48.9 | (41.6, 56.3) | 47.9

Abbreviation: CI, confidence interval.

^1Patients in MMR at the specified time point in the TFR phase.

^2Based on the time to event (loss of MMR) data during the TFR phase.

Among the 190 patients in the TFR phase, 98 patients had a treatment-free survival (TFS) event (defined as discontinuation from TFR phase due to any reason, loss of MMR, death due to any cause, progression to AP/BC up to the end of TFR phase, or reinitiation of treatment due to any cause in the study) by the 96-week cut-off date.

Figure 1: Kaplan-Meier Estimate of Treatment-Free Survival After Start of TFR (Full Analysis Set ENEST freedom)

1. For a given time point, the points on the dashed curves represent the 95% confidence limits for the associated KM estimate on the solid curve.
2. By the time of the 96-week data cut-off date, one single patient lost MMR at Week 120, at the time when only 8 patients were considered at risk. This explains the artificial drop at the end of the curve.

14.4 Treatment Discontinuation in Ph+ CML-CP Patients Who Have Achieved a Sustained Molecular Response (MR4.5) on Nilotinib Capsules Following Prior Imatinib Therapy

The ENESTop (Evaluating Nilotinib Efficacy and Safety in clinical Trials-STop) study (NCT01698905) is an open-label, multicenter, single-arm study, where 163 adult patients with Ph+ CML-CP taking tyrosine kinase inhibitors (TKIs) for ≥ 3 years (imatinib as initial TKI therapy for more than 4 weeks without documented MR4.5 on imatinib at the time of switch to nilotinib, then switched to nilotinib for at least 2 years), and who achieved MR4.5 on nilotinib treatment as measured with the MolecularMD MRDx® BCR-ABL Test were enrolled to continue nilotinib treatment for an additional 52 weeks (nilotinib consolidation phase). Of the 163 patients, 126 patients (77.3%) entered the TFR phase after achieving a sustained molecular response (MR4.5) during the consolidation phase, defined by the following criterion:

- The 4 last quarterly assessments (taken every 12 weeks) showed no confirmed loss of MR4.5 (BCRABL/ABL ≤ 0.0032% IS) during 1 year.

The median age of patients who entered the TFR phase was 56 years, 55.6% were females, and 27.8% of the patients were ≥ 65 years of age. The median actual dose intensity during the 52-week nilotinib consolidation phase was 771.8 mg/day with 52.4%, 29.4%, 0.8%, 16.7%, and 0.8% of patients receiving a daily nilotinib dose of 800 mg, 600 mg, 450 mg, 400 mg and 300 mg just before entry into the TFR phase, respectively.

Patients who entered the TFR phase but experienced two consecutive measurements of BCR-ABL/ABL > 0.01% IS were considered having a confirmed loss of MR4.0, triggering reinitiation of nilotinib treatment. Patients with loss of MMR in the TFR phase immediately restarted nilotinib treatment without confirmation. All patients who restarted nilotinib therapy had BCR-ABL transcript levels monitored every 4 weeks for the first 24 weeks, then once every 12 weeks.

Efficacy was based on the 96-week analysis data cut-off date, by which time, 61 patients (48.4%) had discontinued from the TFR phase: 58 patients (46.0%) due to loss of MMR or confirmed loss of MR4.0, 2 patients (1.6%) due to subject/guardian decision and one patient (0.8%) due to pregnancy. Among the 58 patients who discontinued from the TFR phase due to confirmed loss of MR4.0 or loss of MMR, 56 patients restarted nilotinib therapy and 2 patients permanently discontinued from the study.

By the 96-week data cut-off, of the 56 patients who restarted nilotinib treatment due to confirmed loss of MR4.0 or loss of MMR in the TFR phase, 52 patients (92.9%) regained MR4.0 and MR4.5; 4 patients (7.1%) did not regain MR4.0 by the time of the cut-off date. The cumulative rate of MR4 and MR4.5 regained by 48-weeks since treatment reinitiation, was 92.9% (52/56 patients) and 91.1% (51/56 patients), respectively.

Table 15: Efficacy Results for ENESTop

Patients who entered the treatment free remission (TFR) phase (full analysis set, N = 126)
 | Patients in TFR phase^1 at the specified time point |  | Loss of MMR or confirmed loss of MR4^2 by the specified time point
 | % | 95% CI | %
24 weeks | 60.3 | (51.2, 68.9) | 38.9
48 weeks | 57.9 | (48.8, 66.7) | 41.3
96 weeks | 53.2 | (44.1, 62.1) | 43.7

Abbreviation: CI, confidence interval.

^1Patients without loss of MMR or confirmed loss of MR4 by specified time point of TFR phase.

^2Based on the time to event (loss of MMR or confirmed loss of MR4) data during the TFR phase.

Among the 126 patients in the TFR phase, 61 patients (48.4%) had a treatment-free survival (TFS) event (defined as discontinuation from TFR phase due to any reason, loss of MMR, confirmed loss of MR4, death due to any cause, progression to AP/BC up to the end of TFR phase, or reinitiation of treatment due to any cause in the study) on or before the 96-month cut-off date.

Figure 2: Kaplan-Meier Estimate of Treatment-Free Survival after Start of TFR (Full Analysis Set ENESTop)

1. For a given time point, the points on the dashed curves represent the 95% confidence limits for the associated KM estimate on the solid curve.

Additional pediatric use information is approved for Novartis Pharmaceuticals Corporation’s Tasigna® (nilotinib) capsules. However, due to Novartis Pharmaceuticals Corporation’s marketing exclusivity rights, this drug product is not labeled with that pediatric information.

16 HOW SUPPLIED/STORAGE AND HANDLING

Nilotinib Capsules are supplied as follows:

Capsule Strength | Description | Package Configuration | NDC Code
50 mg | Light yellow colored blend filled in hard gelatin capsule size 4 cap red opaque linear imprinted with 'Cipla' in black ink and body white opaque linear imprinted with ‘030 50 mg’ in black ink. | Bottle of 120 capsules | NDC 76282-788-12
150 mg | Light yellow colored blend filled in hard gelatin capsule size 1, cap red opaque linear imprinted with 'Cipla' in black ink and body red opaque linear imprinted with ‘031 150 mg’ in black ink. | Carton of 4 individual packs of 28 (4 X 7’s) capsules each | NDC 76282-789-58
 |  | Carton of 4 blister packs of 7 capsules | NDC 76282-789-46
 |  | Blister of 7 capsules | NDC 76282-789-45
200 mg | Light yellow colored blend filled in hard gelatin capsule size 0, cap white opaque linear imprinted with ‘Cipla’ in black ink and body white opaque linear imprinted with ‘032 200 mg’ in black ink. | Carton of 4 individual packs of 28 (4 X 7’s) capsules each | NDC 76282-790-58
 |  | Carton of 4 blister packs of 7 capsules | NDC 76282-790-46
 |  | Blister of 7 capsules | NDC 76282-790-45

Nilotinib Capsules should be stored at 20°C to 25°C (68°F to 77°F); excursions permitted between 15°C and 30°C (59°F and 86°F) [see USP Controlled Room Temperature].

17 PATIENT COUNSELING INFORMATION

Advise the patient to read the FDA-approved patient labeling (Medication Guide).

Taking Nilotinib Capsules

Advise patients to take Nilotinib Capsules doses twice daily approximately 12 hours apart. Advise patients to swallow the capsules whole with water and not open the capsules.

Advise patients to take Nilotinib Capsules on an empty stomach. No food should be consumed for at least 2 hours before the dose is taken and for at least 1 hour after the dose is taken. Patients should not consume grapefruit products and other foods that are known to inhibit CYP3A4 at any time during Nilotinib Capsules treatment [see Dosage and Administration (2.1), Drug Interactions (7.1, 7.2)].

If the patient misses a dose of Nilotinib Capsules, the patient should take the next scheduled dose at its regular time. The patient should not take two doses at the same time.

Compliance

Advise patients of the following:

- Continue taking Nilotinib Capsules every day for as long as their doctor tells them.
- This is a long-term treatment.
- Do not change dose or stop taking Nilotinib Capsules without first consulting their doctor.

Myelosuppression

Advise patients that treatment with Nilotinib Capsules can cause serious thrombocytopenia, neutropenia, and anemia. Advise patients to seek immediate medical attention if symptoms suggestive of low blood counts occur, such as fever, chills or other signs of infection, unexplained bleeding or bruising, or unexplained weakness or shortness of breath [see Warnings and Precautions (5.1)].

QT Prolongation

Advise patients that Nilotinib Capsules can cause possibly life-threatening, abnormal heart beat. Advise patients to seek immediate medical attention if symptoms of abnormal heart beat occur, such as feeling light-headed, faint or experiencing an irregular heartbeat [see Warnings and Precautions (5.2)].

Cardiac and Arterial Vascular Occlusive Events

Advise patients that cardiovascular events (including ischemic heart disease, peripheral arterial occlusive disease, and ischemic cerebrovascular events) have been reported. Advise patients to seek immediate medical attention if any symptoms suggestive of a cardiovascular event occur, such as chest or leg pain, numbness or weakness, or problems walking or speaking occur suddenly [see Warnings and Precautions (5.4)].

Pancreatitis and Elevated Serum Lipase

Advise patients that Nilotinib Capsules can increase the risk of pancreatitis and that patients with a previous history of pancreatitis may be at greater risk. Advise patients to seek immediate medical attention if symptoms suggestive of pancreatitis occur, such as sudden stomach area pain with accompanying nausea and vomiting [see Warnings and Precautions (5.5)].

Hepatotoxicity

Advise patients that Nilotinib Capsules can increase the risk of hepatotoxicity and that patients with previous history of liver diseases may be at risk. Advise patients to seek immediate medical attention if any symptoms suggestive of hepatotoxicity occur, such as stomach pain, yellow skin and eyes, and dark-colored urine [see Warnings and Precautions (5.6)].

Tumor Lysis Syndrome

Advise patients that Nilotinib Capsules can cause TLS and to seek immediate medical attention if any symptoms suggestive of TLS occur, such as an abnormal heartbeat or less urine production [see Warnings and Precautions (5.8)].

Hemorrhage

Advise patients that serious hemorrhagic events, including fatal events, have occurred in patients with CML treated with Nilotinib Capsules. Advise patients to seek immediate medical attention if symptoms suggestive of hemorrhage occur, such as uncontrolled bleeding, changes in eyesight, unconsciousness, or sudden headache or sudden confusion in surroundings [see Warnings and Precautions (5.9)].

Fluid Retention

Advise patients that Nilotinib Capsules can cause fluid retention and to seek immediate medical attention if any symptoms suggestive of fluid retention, such as shortness of breath, rapid weight gain, or swelling occur [see Warnings and Precautions (5.13)].

Effects on Growth and Development in Pediatric Patients

Inform pediatric patients and their caregivers of the possibility of developing growth abnormalities. Growth retardation has been reported in pediatric patients treated with nilotinib. Therefore, monitor growth and development in pediatric patients [see Warnings and Precautions (5.14)].

Treatment-Free Remission (TFR)

Advise patients that frequent monitoring is required to detect possible loss of remission if TFR is attempted.

Advise patients that musculoskeletal symptoms, such as muscle pain, pain in extremity, joint pain, bone pain, or spinal pain, may occur more frequently than before treatment discontinuation [see Warnings and Precautions (5.16)].

Embryo-Fetal Toxicity

Advise pregnant women of the potential risk to a fetus. Advise females of reproductive potential to inform their healthcare provider of a known or suspected pregnancy [see Warnings and Precautions (5.15), Use in Specific Populations (8.1)].

Advise females of reproductive potential to use effective contraception during treatment and for 14 days after receiving the last dose of Nilotinib Capsules [see Use in Specific Populations (8.3)].

Lactation

Advise women not to breastfeed during treatment with Nilotinib Capsules and for 14 days after the last dose [see Use in Specific Populations (8.2)].

Drug Interactions

Advise patients that Nilotinib Capsules and certain other medicines, including over the counter medications or herbal supplements (such as St. John’s Wort), can interact with each other [see Drug Interactions (7)].

Manufactured by:

Cipla Ltd.,

Verna- 403722, Goa, India.

Manufactured for:

Exelan Pharmaceuticals, Inc.

Boca Raton, FL 33432

Medication guide

Nilotinib (nye-LOE-ti-nib) Capsules

What is the most important information I should know about Nilotinib Capsules?

Nilotinib Capsules can cause a possible life-threatening heart problem called QTc prolongation. QTc prolongation causes an irregular heartbeat, which may lead to sudden death.

Your healthcare provider should check the electrical activity of your heart with a test called an electrocardiogram (ECG):

- before starting Nilotinib Capsules
- 7 days after starting Nilotinib Capsules

- with any dose changes
- regularly during Nilotinib Capsules treatment

You may lower your chances for having QTc prolongation with Nilotinib Capsules if you:

- Take Nilotinib Capsules on an empty stomach:
- Avoid eating food for at least 2 hours before the dose is taken, and
- Avoid eating food for at least 1 hour after the dose is taken.
- Do not drink grapefruit juice, eat grapefruit, or take supplements containing grapefruit extract during treatment with Nilotinib Capsules. Grapefruit products increase the amount of Nilotinib Capsules in your body.
- Avoid taking other medicines or supplements with Nilotinib Capsules that can also cause QTc prolongation.
- Nilotinib can interact with many medicines and supplements and increase your chance for serious and life-threatening side effects.
- Do not take any other medicine during treatment with Nilotinib Capsules unless your healthcare provider tells you it is okay to do so.
- For more information, see “How should I take Nilotinib Capsules?”

Call your healthcare provider right away if you feel lightheaded, faint, or have an irregular heartbeat during treatment with Nilotinib Capsules. These can be symptoms of QTc prolongation.

See “What are the possible side effects of Nilotinib Capsules?” for more information about side effects.

What is Nilotinib Capsules?

Nilotinib Capsule is a prescription medicine used to treat:

- adults who have been newly diagnosed with a certain type of leukemia called Philadelphia chromosome positive chronic myeloid leukemia (Ph+ CML) in chronic phase.
- adults with chronic phase Ph+ CML or accelerated phase Ph+ CML who:

- are no longer benefiting from other treatments, including imatinib (Gleevec), or
- have taken other treatments, including imatinib (Gleevec), and cannot tolerate them.

It is not known if nilotinib is safe and effective in children younger than 1 year of age with newly diagnosed, resistant, or intolerant Ph+ CML in chronic phase.

The long-term effects of treating children with nilotinib for a long period of time are not known.

Who should not take Nilotinib Capsules?

Do not take if you have:

- low levels of potassium or magnesium in your blood
- long QTc syndrome

Before taking Nilotinib Capsules, tell your healthcare provider about all of your medical conditions, including if you:

- have heart problems
- have had a stroke or other problems due to decreased blood flow to the brain
- have problems with decreased blood flow to your legs
- have irregular heartbeat
- have QTc prolongation or a family history of it
- have liver problems
- have had pancreatitis
- have low blood levels of potassium or magnesium in your blood
- have a severe problem with lactose (milk sugar) or other sugars. Nilotinib Capsules contain lactose. Most people who have mild or moderate lactose intolerance can take Nilotinib Capsules.
- have bleeding problems
- had a surgical procedure involving the removal of the entire stomach (total gastrectomy)
- are pregnant or plan to become pregnant. Nilotinib can harm your unborn baby. Tell your healthcare provider right away if you are pregnant, or if you become pregnant during treatment with Nilotinib Capsules.

In females who are able to become pregnant:

- Your healthcare provider should do a pregnancy test before you start treatment with Nilotinib Capsules.
- Use effective birth control (contraception) during treatment with Nilotinib Capsules and for 14 days after the last dose.
- are breastfeeding or plan to breastfeed. It is not known if nilotinib passes into your breast milk. Do not breastfeed during treatment and for 14 days after your last dose of Nilotinib Capsules.

Tell your healthcare provider about all the medicines you take, including prescription and over-the-counter medicines, vitamins and herbal supplements.

If you need to take antacids (medicines to treat heartburn) do not take them at the same time that you take Nilotinib Capsules. If you take:

- a medicine to block the amount of acid produced in the stomach (H2 blocker): Take these medicines about 10 hours before you take Nilotinib Capsules, or about 2 hours after you take Nilotinib Capsules.
- an antacid that contains aluminum hydroxide, magnesium hydroxide, and simethicone to reduce the amount of acid in the stomach: Take these medicines about 2 hours before or about 2 hours after you take Nilotinib Capsules.

Nilotinib can interact with many medicines and supplements and increase your chance for serious and life-threatening side effects. See “What is the most important information I should know about Nilotinib Capsules?”

How should I take Nilotinib Capsules?

- Take Nilotinib Capsules exactly as your healthcare provider tells you to take it.
- Do not change your dose or stop taking Nilotinib Capsules unless your healthcare provider tells you.
- Nilotinib Capsules is a long-term treatment.
- Take your prescribed dose of Nilotinib Capsules 2 times a day, about 12 hours apart.
- Your healthcare provider will tell you how many Nilotinib Capsules to take and when to take them.
- Nilotinib Capsules must be taken on an empty stomach.
- Avoid eating food for at least 2 hours before the dose is taken, and
- Avoid eating food for at least 1 hour after the dose is taken.
- Swallow Nilotinib Capsules whole with water. Do not open Nilotinib Capsules. If you cannot swallow Nilotinib Capsules whole, tell your healthcare provider.
- Do not drink grapefruit juice, eat grapefruit, or take supplements containing grapefruit extract at any time during treatment. See “What is the most important information I should know about Nilotinib Capsules?”
- If you miss a dose, just take your next dose at your regular time. Do not take 2 doses at the same time to make up for a missed dose.
- If you take too much Nilotinib Capsules, call your healthcare provider or go to the nearest hospital emergency room right away. Symptoms may include vomiting and drowsiness.
- During treatment with Nilotinib Capsules your healthcare provider will do tests to check for side effects and to see how well Nilotinib Capsules is working for you. The tests will check your:
- heart
- blood cells (white blood cells, red blood cells, and platelets). Your blood cells should be checked every 2 weeks for the first 2 months and then monthly.
- electrolytes (potassium, magnesium)
- pancreas and liver function
- bone marrow samples

Your healthcare provider may change your dose. Your healthcare provider may have you stop Nilotinib Capsules for some time or lower your dose if you have side effects with it.

- Your healthcare provider will monitor your CML during treatment with Nilotinib Capsules to see if you are in a remission. After at least 3 years of treatment with Nilotinib Capsules, your healthcare provider may do certain tests to determine if you continue to be in remission. Based on your test results, your healthcare provider may decide if you may be eligible to try stopping treatment with Nilotinib Capsules. This is called Treatment Free Remission (TFR).
- Your healthcare provider will carefully monitor your CML during and after you stop taking Nilotinib Capsules. Based on your test results, your healthcare provider may need to re-start your Nilotinib Capsules if your CML is no longer in remission.
- It is important that you are followed by your healthcare provider and undergo frequent monitoring to find out if you need to re-start your Nilotinib Capsules treatment because you are no longer in TFR. Follow your healthcare provider’s instructions about re-starting Nilotinib Capsules if you are no longer in TFR.

What are the possible side effects of Nilotinib Capsules?

Nilotinib Capsules may cause serious side effects, including:

- See “What is the most important information I should know about Nilotinib Capsules?”
- Low blood cell counts. Low blood cell counts (red blood cells, white blood cells, and platelets) are common with Nilotinib Capsules, but can also be severe. Your healthcare provider will check your blood counts regularly during treatment with Nilotinib Capsules. Call your healthcare provider or get medical help right away if you develop any signs or symptoms of low blood counts, including:

- fever
- chills or other signs of infection
- unexplained bleeding or bruising
- unexplained weakness
- shortness of breath

- Decreased blood flow to the leg, heart, or brain. People who have recently been diagnosed with Ph+ CML and take Nilotinib Capsules may develop decreased blood flow to the leg, the heart, or brain.

Get medical help right away if you suddenly develop any of the following symptoms:

- chest pain or discomfort
- numbness or weakness
- problems walking or speaking
- leg pain
- your leg feels cold
- change in the skin color of your leg

- Pancreas inflammation (pancreatitis). Tell your healthcare provider right away if you develop any symptoms of pancreatitis, including sudden stomach area pain with nausea and vomiting.
- Liver problems. Nilotinib Capsules can increase your risk of liver problems. People who have had liver problems in the past may be at risk for getting liver problems with Nilotinib Capsules. Call your healthcare provider or get medical help right away if you develop any symptoms of liver problems, including:

- stomach area (abdominal) pain

- yellow skin and eyes

- dark-colored urine

- Tumor Lysis Syndrome (TLS). TLS is caused by a fast breakdown of cancer cells. Your healthcare provider may do blood tests to check you for TLS. TLS can cause you to have:

- kidney failure and the need for dialysis treatment
- an abnormal heart beat

- Bleeding problems. Serious bleeding problems and death have happened during treatment with Nilotinib Capsules. Tell your healthcare provider right away if you develop any signs and symptoms of bleeding during treatment with Nilotinib Capsules.
- Fluid retention. Your body may hold too much fluid (fluid retention). Symptoms of fluid retention include shortness of breath, rapid weight gain, and swelling.
- Abnormal growth or development in children. Effects on growth and development have happened in children with chronic phase Ph+ CML during treatment with nilotinib. Some children and adolescents may have slower than normal growth during treatment with nilotinib.

The most common side effects of Nilotinib Capsules in adults include:

- nausea
- rash
- headache
- tiredness
- itching
- vomiting

- diarrhea
- cough
- constipation
- muscle and joint pain
- runny or stuffy nose, sneezing, sore throat
- fever
- night sweat

Side effects in adults attempting treatment free remission:

If you and your healthcare provider decide that you can stop taking Nilotinib Capsules and try treatment free remission (TFR), you may have more muscle and bone (musculoskeletal) symptoms than before you stopped treatment. Symptoms may include:

- muscle pain
- arm and leg pain
- joint pain

- bone pain
- spine pain

Tell your healthcare provider if you have any side effect that bothers you or does not go away.

These are not all of the possible side effects of Nilotinib Capsules.

Call your doctor for medical advice about side effects. You may report side effects to FDA at 1-800-FDA-1088.

How should I store Nilotinib Capsules?

- Store Nilotinib Capsules at room temperature between 68°F to 77°F (20°C to 25°C).
- Safely throw away medicine that is out of date or no longer needed.

Keep Nilotinib Capsules and all medicines out of the reach of children.

General information about the safe and effective use of Nilotinib Capsules.

Medicines are sometimes prescribed for purposes other than those listed in a Medication Guide. Do not use Nilotinib Capsules for a condition for which it was not prescribed. Do not give Nilotinib Capsules to other people, even if they have the same symptoms that you have. It may harm them. You can ask your pharmacist or healthcare provider for information about Nilotinib Capsules that is written for health professionals.

What are the ingredients in Nilotinib Capsules?

Active ingredient: nilotinib d-tartrate

Inactive ingredients: colloidal silicon dioxide, crospovidone, lactose monohydrate, magnesium aluminometasilicate, magnesium stearate and polysorbate 80.

The empty capsules contain gelatin, iron oxide (black), iron oxide (red), iron oxide (yellow), and titanium dioxide. The black ink contains iron oxide (black), potassium hydroxide, propylene glycol, shellac, and strong ammonia solution.

Manufactured by:

Cipla Ltd.,

Verna- 403722, Goa, India.

Manufactured for:

Exelan Pharmaceuticals, Inc.

Boca Raton, FL 33432

For more information call 1-866-604-3268.

Additional pediatric use information is approved for Novartis Pharmaceuticals Corporation’s Tasigna® (nilotinib) capsules. However, due to Novartis Pharmaceuticals Corporation’s marketing exclusivity rights, this drug product is not labeled with that pediatric information.

This Medication Guide has been approved by the U.S. Food and Drug Administration.

Issued: 10/2025

PACKAGE LABEL. PRINCIPAL DISPLAY PANEL

NDC 76282-788-12

Nilotinib Capsules

50 mg

Dispense with Medication Guide

Exelan Pharmaceuticals, Inc.

Rx Only 120 Capsules

NDC 76282-789-58

Nilotinib Capsules

150 mg per capsule

PHARMACIST:

DISPENSE WITH MEDICATION GUIDE ATTACHED OR PROVIDED SEPARATELY.

TAKE NILOTINIB CAPSULES ON EMPTY STOMACH. AVOID FOOD FOR

AT LEAST 2 HOURS BEFORE TAKING A DOSE OF NILOTINIB CAPSULES

AND AT LEAST 1 HOUR AFTER THE DOSE IS TAKEN.

Exelan Pharmaceuticals, Inc.

Rx Only

Contents: 112 capsules (4 individual packs

containing 28 capsules each).

NDC 76282-790-58

Nilotinib Capsules

200 mg per capsule

PHARMACIST:

DISPENSE WITH MEDICATION GUIDE ATTACHED OR PROVIDED SEPARATELY.

TAKE NILOTINIB CAPSULES ON EMPTY STOMACH. AVOID FOOD FOR

AT LEAST 2 HOURS BEFORE TAKING A DOSE OF NILOTINIB CAPSULES

AND AT LEAST 1 HOUR AFTER THE DOSE IS TAKEN.

Exelan Pharmaceuticals, Inc.

Rx Only

Contents: 112 capsules (4 individual packs

containing 28 capsules each).